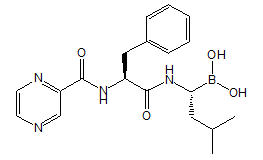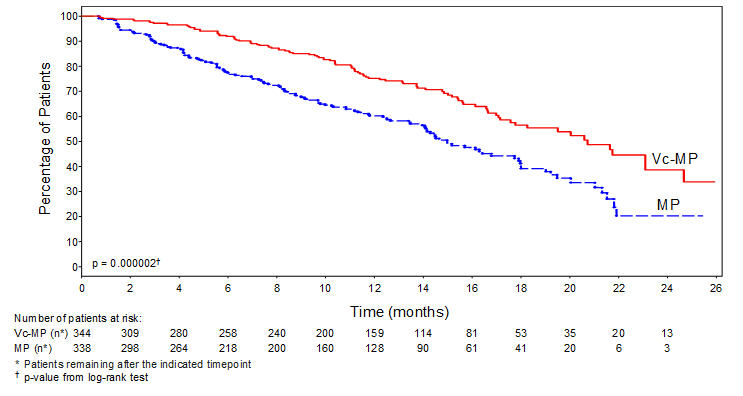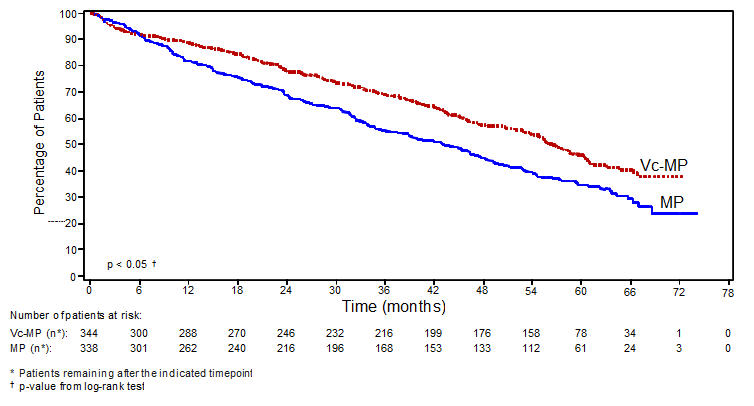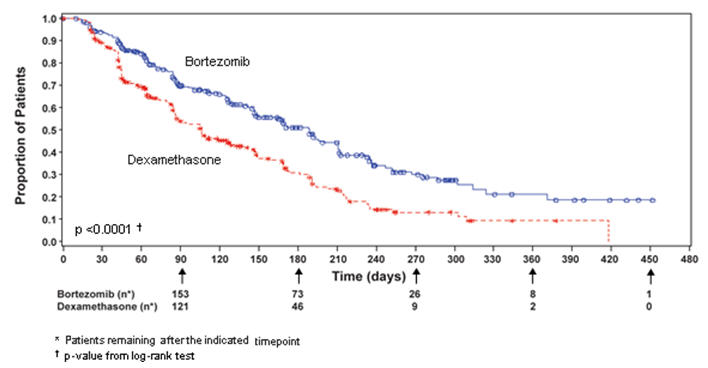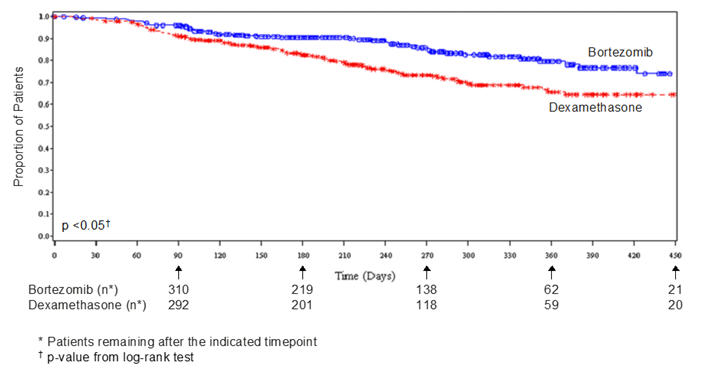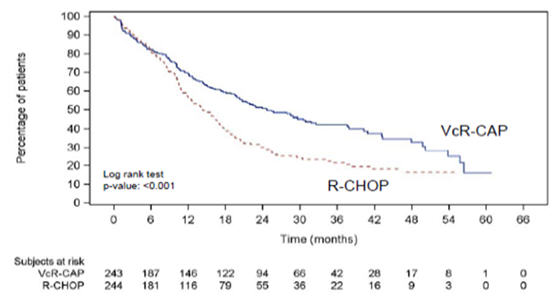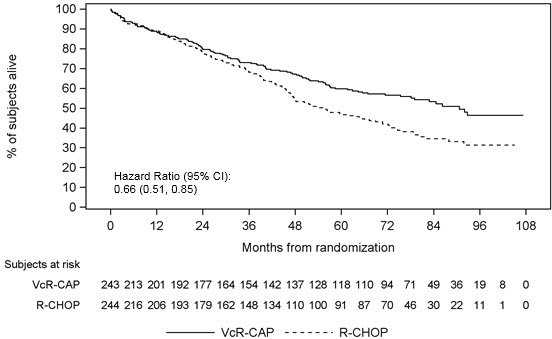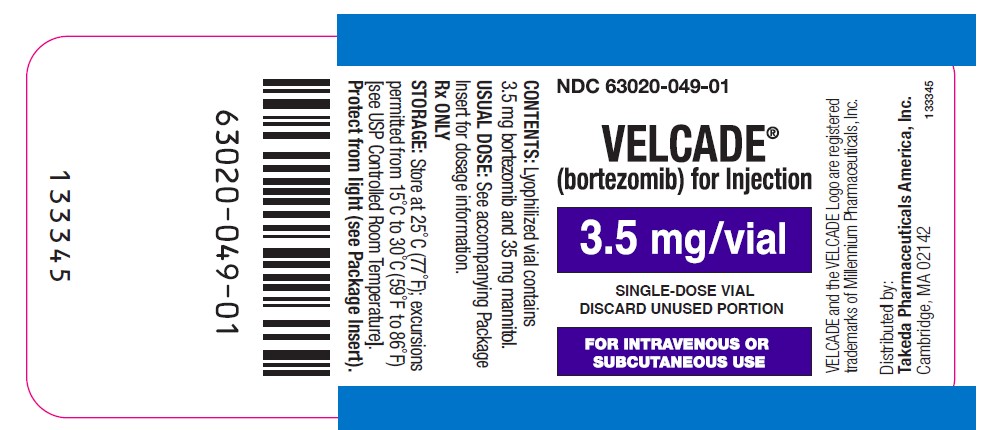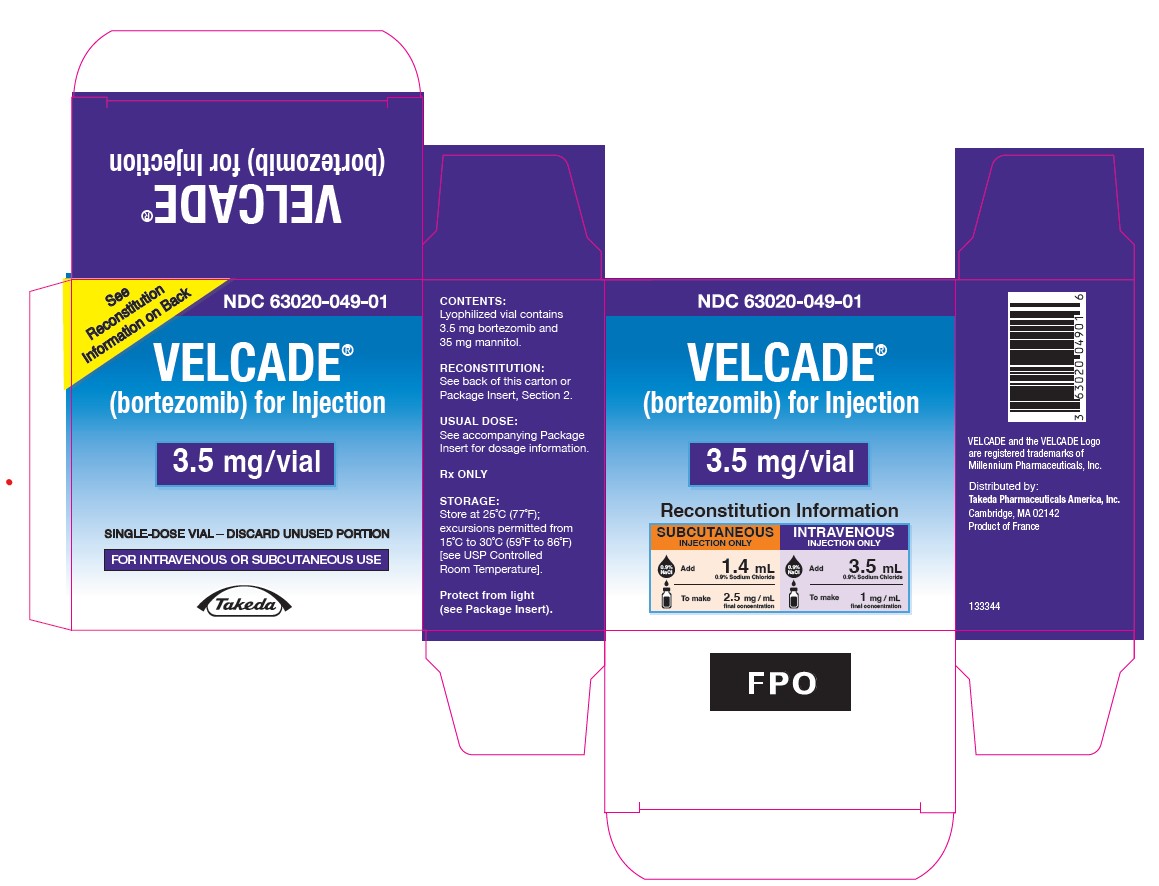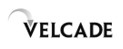 DRUG LABEL: VELCADE
NDC: 63020-049 | Form: INJECTION, POWDER, LYOPHILIZED, FOR SOLUTION
Manufacturer: Takeda Pharmaceuticals America, Inc.
Category: prescription | Type: HUMAN PRESCRIPTION DRUG LABEL
Date: 20250828

ACTIVE INGREDIENTS: bortezomib 3.5 mg/1 1
INACTIVE INGREDIENTS: mannitol

HIGHLIGHTS OF PRESCRIBING INFORMATION

These highlights do not include all the information needed to use VELCADE safely and effectively. See full prescribing information for VELCADE.
VELCADE® (bortezomib) for injection, for subcutaneous or intravenous use
Initial U.S. Approval: 2003

1 INDICATIONS AND USAGE

VELCADE is a proteasome inhibitor indicated for:

- treatment of adult patients with multiple myeloma (1.1)
- treatment of adult patients with mantle cell lymphoma (1.2)

2 DOSAGE AND ADMINISTRATION

- For subcutaneous or intravenous use only. Each route of administration has a different reconstituted concentration. Exercise caution when calculating the volume to be administered. (2.1, 2.10)
- The recommended starting dose of VELCADE is 1.3 mg/m^2 administered either as a 3 to 5 second bolus intravenous injection or subcutaneous injection. (2.2, 2.4, 2.6)
- Retreatment for Multiple Myeloma: May retreat starting at the last tolerated dose. (2.6)
- Hepatic Impairment: Use a lower starting dose for patients with moderate or severe hepatic impairment. (2.8)
- Dose must be individualized to prevent overdose. (2.10)

3 DOSAGE FORMS AND STRENGTHS

For injection: Single-dose vial contains 3.5 mg of bortezomib as lyophilized powder for reconstitution and withdrawal of the appropriate individual patient dose. (3)

4 CONTRAINDICATIONS

- Patients with hypersensitivity (not including local reactions) to bortezomib, boron, or mannitol, including anaphylactic reactions. (4)
- Contraindicated for intrathecal administration. (4)

5 WARNINGS AND PRECAUTIONS

- Peripheral Neuropathy: Manage with dose modification or discontinuation. (2.7) Patients with pre-existing severe neuropathy should be treated with VELCADE only after careful risk-benefit assessment. (2.7, 5.1)
- Hypotension: Use caution when treating patients taking antihypertensives, with a history of syncope, or with dehydration. (5.2)
- Cardiac Toxicity: Worsening of and development of cardiac failure has occurred. Closely monitor patients with existing heart disease or risk factors for heart disease. (5.3)
- Pulmonary Toxicity: Acute respiratory syndromes have occurred. Monitor closely for new or worsening symptoms and consider interrupting VELCADE therapy. (5.4)
- Posterior Reversible Encephalopathy Syndrome: Consider MRI imaging for onset of visual or neurological symptoms; discontinue VELCADE if suspected. (5.5)
- Gastrointestinal Toxicity: Nausea, diarrhea, constipation, and vomiting may require use of antiemetic and antidiarrheal medications or fluid replacement. (5.6)
- Thrombocytopenia and Neutropenia: Monitor complete blood counts regularly throughout treatment. (5.7)
- Tumor Lysis Syndrome: Closely monitor patients with high tumor burden. (5.8)
- Hepatic Toxicity: Monitor hepatic enzymes during treatment. Interrupt VELCADE therapy to assess reversibility. (5.9)
- Thrombotic Microangiopathy: Monitor for signs and symptoms. Discontinue VELCADE if suspected. (5.10)
- Embryo-Fetal Toxicity: VELCADE can cause fetal harm. Advise females of reproductive potential and males with female partners of reproductive potential of the potential risk to a fetus and to use effective contraception. (5.11)

6 ADVERSE REACTIONS

Most commonly reported adverse reactions (incidence ≥20%) in clinical studies include nausea, diarrhea, thrombocytopenia, neutropenia, peripheral neuropathy, fatigue, neuralgia, anemia, leukopenia, constipation, vomiting, lymphopenia, rash, pyrexia, and anorexia. (6.1)

To report SUSPECTED ADVERSE REACTIONS, contact Takeda Pharmaceuticals at 1-866-VELCADE or FDA at 1-800-FDA-1088 or www.fda.gov/medwatch.

7 DRUG INTERACTIONS

- Strong CYP3A4 Inhibitors: Closely monitor patients with concomitant use. (7.1)
- Strong CYP3A4 Inducers: Avoid concomitant use. (7.1)

8 USE IN SPECIFIC POPULATIONS

Patients with diabetes may require close monitoring of blood glucose and adjustment of antidiabetic medication. (8.8)

FULL PRESCRIBING INFORMATION

1 INDICATIONS AND USAGE

1.1 Multiple Myeloma

VELCADE is indicated for the treatment of adult patients with multiple myeloma.

1.2 Mantle Cell Lymphoma

VELCADE is indicated for the treatment of adult patients with mantle cell lymphoma.

2 DOSAGE AND ADMINISTRATION

2.1 Important Dosing Guidelines

VELCADE is for intravenous or subcutaneous use only. Do not administer VELCADE by any other route.

Because each route of administration has a different reconstituted concentration, use caution when calculating the volume to be administered.

The recommended starting dose of VELCADE is 1.3 mg/m^2. VELCADE is administered intravenously at a concentration of 1 mg/mL, or subcutaneously at a concentration of 2.5 mg/mL [see Dosage and Administration (2.10)].

VELCADE retreatment may be considered for patients with multiple myeloma who had previously responded to treatment with VELCADE and who have relapsed at least six months after completing prior VELCADE treatment. Treatment may be started at the last tolerated dose [see Dosage and Administration (2.6)].

When administered intravenously, administer VELCADE as a 3 to 5 second bolus intravenous injection.

2.2 Dosage in Previously Untreated Multiple Myeloma

VELCADE is administered in combination with oral melphalan and oral prednisone for 9, six week treatment cycles as shown in Table 1. In Cycles 1 to 4, VELCADE is administered twice weekly (Days 1, 4, 8, 11, 22, 25, 29 and 32). In Cycles 5 to 9, VELCADE is administered once weekly (Days 1, 8, 22 and 29). At least 72 hours should elapse between consecutive doses of VELCADE.

Table 1: Dosage Regimen for Patients with Previously Untreated Multiple Myeloma
Twice Weekly VELCADE (Cycles 1 to 4)
Week | 1 |  |  |  | 2 |  | 3 | 4 |  | 5 |  | 6
VELCADE (1.3 mg/m^2) | Day 1 | -- | -- | Day 4 | Day 8 | Day 11 | rest period | Day 22 | Day 25 | Day 29 | Day 32 | rest period
Melphalan (9 mg/m^2) Prednisone (60 mg/m^2) | Day 1 | Day 2 | Day 3 | Day 4 | -- | -- | rest period | -- | -- | -- | -- | rest period
Once Weekly VELCADE (Cycles 5 to 9 when used in combination with Melphalan and Prednisone)
Week | 1 |  |  |  | 2 |  | 3 | 4 |  | 5 |  | 6
VELCADE (1.3 mg/m^2) | Day 1 | -- | -- |  | Day 8 |  | rest period | Day 22 |  | Day 29 |  | rest period
Melphalan (9 mg/m^2) Prednisone (60 mg/m^2) | Day 1 | Day 2 | Day 3 | Day 4 | -- | -- | rest period | -- | -- | -- | -- | rest period

2.3 Dose Modification Guidelines for VELCADE When Given in Combination with Melphalan and Prednisone

Prior to initiating any cycle of therapy with VELCADE in combination with melphalan and prednisone:

- Platelet count should be at least 70 × 10^9/L and the absolute neutrophil count (ANC) should be at least 1 × 10^9/L
- Nonhematological toxicities should have resolved to Grade 1 or baseline

Table 2: Dose Modifications During Cycles of Combination VELCADE, Melphalan and Prednisone Therapy
Toxicity | Dose Modification or Delay
Hematological toxicity during a cycle: If prolonged Grade 4 neutropenia or thrombocytopenia, or thrombocytopenia with bleeding is observed in the previous cycle | Consider reduction of the melphalan dose by 25% in the next cycle
If platelet count is not above 30 × 10^9/L or ANC is not above 0.75 × 10^9/L on a VELCADE dosing day (other than Day 1) | Withhold VELCADE dose
If several VELCADE doses in consecutive cycles are withheld due to toxicity | Reduce VELCADE dose by one dose level (from 1.3 mg/m^2 to 1 mg/m^2, or from 1 mg/m^2 to 0.7 mg/m^2)
Grade 3 or higher nonhematological toxicities | Withhold VELCADE therapy until symptoms of toxicity have resolved to Grade 1 or baseline. Then, VELCADE may be reinitiated with one dose level reduction (from 1.3 mg/m^2 to 1 mg/m^2, or from 1 mg/m^2 to 0.7 mg/m^2). For VELCADE-related neuropathic pain and/or peripheral neuropathy, hold or modify VELCADE as outlined in Table 5.

For information concerning melphalan and prednisone, see manufacturer's prescribing information.

Dose modifications guidelines for peripheral neuropathy are provided [see Dosage and Administration (2.7)].

2.4 Dosage in Previously Untreated Mantle Cell Lymphoma

VELCADE (1.3 mg/m^2) is administered intravenously in combination with intravenous rituximab, cyclophosphamide, doxorubicin and oral prednisone (VcR-CAP) for 6, three week treatment cycles as shown in Table 3. VELCADE is administered first followed by rituximab. VELCADE is administered twice weekly for two weeks (Days 1, 4, 8, and 11) followed by a ten day rest period on Days 12 to 21. For patients with a response first documented at Cycle 6, two additional VcR-CAP cycles are recommended. At least 72 hours should elapse between consecutive doses of VELCADE.

Table 3: Dosage Regimen for Patients with Previously Untreated Mantle Cell Lymphoma
Twice Weekly VELCADE (6, Three Week Cycles) [Dosing may continue for two more cycles (for a total of eight cycles) if response is first seen at Cycle 6.]
Week | 1 |  |  |  |  | 2 |  | 3
VELCADE (1.3 mg/m^2) | Day 1 | -- | -- | Day 4 | -- | Day 8 | Day 11 | rest period
Rituximab (375 mg/m^2) Cyclophosphamide (750 mg/m^2) Doxorubicin (50 mg/m^2) | Day 1 | -- | -- |  |  | -- | -- | rest period
Prednisone (100 mg/m^2) | Day 1 | Day 2 | Day 3 | Day 4 | Day 5 | -- | -- | rest period

2.5 Dose Modification Guidelines for VELCADE When Given in Combination with Rituximab, Cyclophosphamide, Doxorubicin and Prednisone

Prior to the first day of each cycle (other than Cycle 1):

- Platelet count should be at least 100 × 10^9/L and absolute neutrophil count (ANC) should be at least 1.5 × 10^9/L
- Hemoglobin should be at least 8 g/dL (at least 4.96 mmol/L)
- Nonhematologic toxicity should have recovered to Grade 1 or baseline

Interrupt VELCADE treatment at the onset of any Grade 3 hematologic or nonhematological toxicities, excluding neuropathy [see Table 5, Warnings and Precautions (5)]. For dose adjustments, see Table 4 below.

Table 4: Dose Modifications on Days 4, 8, and 11 During Cycles of Combination VELCADE, Rituximab, Cyclophosphamide, Doxorubicin and Prednisone Therapy
Toxicity | Dose Modification or Delay
Hematological Toxicity
- Grade 3 or higher neutropenia, or a platelet count not at or above 25 × 10^9/L | Withhold VELCADE therapy for up to 2 weeks until the patient has an ANC at or above 0.75 × 10^9/L and a platelet count at or above 25 × 10^9/L.; - If, after VELCADE has been withheld, the toxicity does not resolve, discontinue VELCADE. - If toxicity resolves such that the patient has an ANC at or above 0.75 × 10^9/L and a platelet count at or above 25 × 10^9/L, VELCADE dose should be reduced by 1 dose level (from 1.3 mg/m^2 to 1 mg/m^2, or from 1 mg/m^2 to 0.7 mg/m^2).
Grade 3 or higher nonhematological toxicities | Withhold VELCADE therapy until symptoms of the toxicity have resolved to Grade 2 or better. Then, VELCADE may be reinitiated with one dose level reduction (from 1.3 mg/m^2 to 1 mg/m^2, or from 1 mg/m^2 to 0.7 mg/m^2). For VELCADE-related neuropathic pain and/or peripheral neuropathy, hold or modify VELCADE as outlined in Table 5.

For information concerning rituximab, cyclophosphamide, doxorubicin and prednisone, see manufacturer's prescribing information.

2.6 Dosage and Dose Modifications for Relapsed Multiple Myeloma and Relapsed Mantle Cell Lymphoma

VELCADE (1.3 mg/m^2/dose) is administered twice weekly for two weeks (Days 1, 4, 8, and 11) followed by a ten day rest period (Days 12 to 21). For extended therapy of more than eight cycles, VELCADE may be administered on the standard schedule or, for relapsed multiple myeloma, on a maintenance schedule of once weekly for four weeks (Days 1, 8, 15, and 22) followed by a 13 day rest period (Days 23 to 35) [see Clinical Studies (14)]. At least 72 hours should elapse between consecutive doses of VELCADE.

Patients with multiple myeloma who have previously responded to treatment with VELCADE (either alone or in combination) and who have relapsed at least six months after their prior VELCADE therapy may be started on VELCADE at the last tolerated dose. Retreated patients are administered VELCADE twice weekly (Days 1, 4, 8, and 11) every three weeks for a maximum of eight cycles. At least 72 hours should elapse between consecutive doses of VELCADE. VELCADE may be administered either as a single agent or in combination with dexamethasone [see Clinical Studies (14.1)].

VELCADE therapy should be withheld at the onset of any Grade 3 nonhematological or Grade 4 hematological toxicities excluding neuropathy as discussed below [see Warnings and Precautions (5)]. Once the symptoms of the toxicity have resolved, VELCADE therapy may be reinitiated at a 25% reduced dose (1.3 mg/m^2/dose reduced to 1 mg/m^2/dose; 1 mg/m^2/dose reduced to 0.7 mg/m^2/dose).

For dose modifications guidelines for peripheral neuropathy, see section 2.7.

2.7 Dose Modifications for Peripheral Neuropathy

Starting VELCADE subcutaneously may be considered for patients with pre-existing or at high risk of peripheral neuropathy. Patients with pre-existing severe neuropathy should be treated with VELCADE only after careful risk-benefit assessment.

Patients experiencing new or worsening peripheral neuropathy during VELCADE therapy may require a decrease in the dose and/or a less dose-intense schedule.

For dose or schedule modification guidelines for patients who experience VELCADE-related neuropathic pain and/or peripheral neuropathy, see Table 5.

Table 5: Recommended Dose Modification for VELCADE-Related Neuropathic Pain and/or Peripheral Sensory or Motor Neuropathy
Severity of Peripheral Neuropathy Signs and Symptoms [Grading based on NCI Common Terminology Criteria CTCAE v4.0] | Modification of Dose and Regimen
Grade 1 (asymptomatic; loss of deep tendon reflexes or paresthesia) without pain or loss of function | No action
Grade 1 with pain or Grade 2 (moderate symptoms; limiting instrumental Activities of Daily Living (ADL) [Instrumental ADL: refers to preparing meals, shopping for groceries or clothes, using telephone, managing money, etc.]) | Reduce VELCADE to 1 mg/m^2
Grade 2 with pain or Grade 3 (severe symptoms; limiting self care ADL [Self care ADL: refers to bathing, dressing and undressing, feeding self, using the toilet, taking medications, and not bedridden]) | Withhold VELCADE therapy until toxicity resolves. When toxicity resolves reinitiate with a reduced dose of VELCADE at 0.7 mg/m^2 once per week.
Grade 4 (life-threatening consequences; urgent intervention indicated) | Discontinue VELCADE

2.8 Dosage in Patients with Hepatic Impairment

Do not adjust the starting dose for patients with mild hepatic impairment.

Start patients with moderate or severe hepatic impairment at a reduced dose of 0.7 mg/m^2 per injection during the first cycle, and consider subsequent dose escalation to 1 mg/m^2 or further dose reduction to 0.5 mg/m^2 based on patient tolerance (see Table 6) [see Use in Specific Populations (8.7), Clinical Pharmacology (12.3)].

Table 6: Recommended Starting Dose Modification for VELCADE in Patients with Hepatic Impairment
 | Bilirubin Level | SGOT (AST) Levels | Modification of Starting Dose
Mild | Less than or equal to 1× ULN | More than ULN | None
Mild | More than 1× to 1.5× ULN | Any | None
Moderate | More than 1.5× to 3× ULN | Any | Reduce VELCADE to 0.7 mg/m^2 in the first cycle. Consider dose escalation to 1 mg/m^2 or further dose reduction to 0.5 mg/m^2 in subsequent cycles based on patient tolerability.
Severe | More than 3× ULN | Any | Reduce VELCADE to 0.7 mg/m^2 in the first cycle. Consider dose escalation to 1 mg/m^2 or further dose reduction to 0.5 mg/m^2 in subsequent cycles based on patient tolerability.
Abbreviations: SGOT = serum glutamic oxaloacetic transaminase;
AST = aspartate aminotransferase; ULN = upper limit of the normal range.

2.9 Administration Precautions

The drug quantity contained in one vial (3.5 mg) may exceed the usual dose required. Caution should be used in calculating the dose to prevent overdose [see Dosage and Administration (2.10)].

When administered subcutaneously, sites for each injection (thigh or abdomen) should be rotated. New injections should be given at least one inch from an old site and never into areas where the site is tender, bruised, erythematous, or indurated.

If local injection site reactions occur following VELCADE administration subcutaneously, a less concentrated VELCADE solution (1 mg/mL instead of 2.5 mg/mL) may be administered subcutaneously [see Dosage and Administration (2.10)]. Alternatively, consider use of the intravenous route of administration [see Dosage and Administration (2.10)].

VELCADE is a hazardous drug. Follow applicable special handling and disposal procedures.^1

2.10 Reconstitution/Preparation for Intravenous and Subcutaneous Administration

Use proper aseptic technique. Reconstitute only with 0.9% sodium chloride. The reconstituted product should be a clear and colorless solution.

Different volumes of 0.9% sodium chloride are used to reconstitute the product for the different routes of administration. The reconstituted concentration of bortezomib for subcutaneous administration (2.5 mg/mL) is greater than the reconstituted concentration of bortezomib for intravenous administration (1 mg/mL). Because each route of administration has a different reconstituted concentration, use caution when calculating the volume to be administered [see Dosage and Administration (2.9)].

For each 3.5 mg single-dose vial of bortezomib, reconstitute with the following volume of 0.9% sodium chloride based on route of administration (Table 7):

Table 7: Reconstitution Volumes and Final Concentration for Intravenous and Subcutaneous Administration
Route of Administration | Bortezomib (mg/vial) | Diluent (0.9% Sodium Chloride) | Final Bortezomib Concentration (mg/mL)
Intravenous | 3.5 mg | 3.5 mL | 1 mg/mL
Subcutaneous | 3.5 mg | 1.4 mL | 2.5 mg/mL

Dose must be individualized to prevent overdosage. After determining patient body surface area (BSA) in square meters, use the following equations to calculate the total volume (mL) of reconstituted VELCADE to be administered:

- Intravenous Administration [1 mg/mL concentration]
  VELCADE dose (mg/m^2) × patient BSA (m^2) | =Total VELCADE volume (mL) to be administered
  1 mg/mL | =Total VELCADE volume (mL) to be administered
- Subcutaneous Administration [2.5 mg/mL concentration]
  VELCADE dose (mg/m^2) × patient BSA (m^2) | =Total VELCADE volume (mL) to be administered
  2.5 mg/mL | =Total VELCADE volume (mL) to be administered

Stickers that indicate the route of administration are provided with each VELCADE vial. These stickers should be placed directly on the syringe of VELCADE once VELCADE is prepared to help alert practitioners of the correct route of administration for VELCADE.

Parenteral drug products should be inspected visually for particulate matter and discoloration prior to administration whenever solution and container permit. If any discoloration or particulate matter is observed, the reconstituted product should not be used.

Stability

Unopened vials of VELCADE are stable until the date indicated on the package when stored in the original package protected from light.

VELCADE contains no antimicrobial preservative. Administer reconstituted VELCADE within eight hours of preparation. When reconstituted as directed, VELCADE may be stored at 25°C (77°F). The reconstituted material may be stored in the original vial and/or the syringe prior to administration. The product may be stored for up to eight hours in a syringe; however, total storage time for the reconstituted material must not exceed eight hours when exposed to normal indoor lighting.

3 DOSAGE FORMS AND STRENGTHS

For injection: Each single-dose vial of VELCADE contains 3.5 mg of bortezomib as a sterile lyophilized white to off-white powder for reconstitution and withdrawal of the appropriate individual patient dose [see Dosage and Administration (2.10)].

4 CONTRAINDICATIONS

VELCADE is contraindicated in patients with hypersensitivity (not including local reactions) to bortezomib, boron, or mannitol. Reactions have included anaphylactic reactions [see Adverse Reactions (6.1)].

VELCADE is contraindicated for intrathecal administration. Fatal events have occurred with intrathecal administration of VELCADE.

5 WARNINGS AND PRECAUTIONS

5.1 Peripheral Neuropathy

VELCADE treatment causes a peripheral neuropathy that is predominantly sensory; however, cases of severe sensory and motor peripheral neuropathy have been reported. Patients with pre-existing symptoms (numbness, pain or a burning feeling in the feet or hands) and/or signs of peripheral neuropathy may experience worsening peripheral neuropathy (including ≥Grade 3) during treatment with VELCADE. Patients should be monitored for symptoms of neuropathy, such as a burning sensation, hyperesthesia, hypoesthesia, paresthesia, discomfort, neuropathic pain or weakness. In the Phase 3 relapsed multiple myeloma trial comparing VELCADE subcutaneous vs intravenous, the incidence of Grade ≥2 peripheral neuropathy was 24% for subcutaneous and 39% for intravenous. Grade ≥3 peripheral neuropathy occurred in 6% of patients in the subcutaneous treatment group, compared with 15% in the intravenous treatment group [see Adverse Reactions (6.1)]. Starting VELCADE subcutaneously may be considered for patients with pre-existing or at high risk of peripheral neuropathy.

Patients experiencing new or worsening peripheral neuropathy during VELCADE therapy may require a decrease in the dose and/or a less dose-intense schedule [see Dosage and Administration (2.7)]. In the VELCADE vs dexamethasone Phase 3 relapsed multiple myeloma study, improvement in or resolution of peripheral neuropathy was reported in 48% of patients with ≥Grade 2 peripheral neuropathy following dose adjustment or interruption. Improvement in or resolution of peripheral neuropathy was reported in 73% of patients who discontinued due to Grade 2 neuropathy or who had ≥Grade 3 peripheral neuropathy in the Phase 2 multiple myeloma studies. The long-term outcome of peripheral neuropathy has not been studied in mantle cell lymphoma.

5.2 Hypotension

The incidence of hypotension (postural, orthostatic, and hypotension NOS) was 8% [see Adverse Reactions (6.1)]. These events are observed throughout therapy. Patients with a history of syncope, patients receiving medications known to be associated with hypotension, and patients who are dehydrated may be at increased risk of hypotension. Management of orthostatic/postural hypotension may include adjustment of antihypertensive medications, hydration, and administration of mineralocorticoids and/or sympathomimetics.

5.3 Cardiac Toxicity

Acute development or exacerbation of congestive heart failure and new onset of decreased left ventricular ejection fraction have occurred during VELCADE therapy, including reports in patients with no risk factors for decreased left ventricular ejection fraction [see Adverse Reactions (6.1)]. Patients with risk factors for, or existing heart disease should be frequently monitored. In the relapsed multiple myeloma study of VELCADE vs dexamethasone, the incidence of any treatment-related cardiac disorder was 8% and 5% in the VELCADE and dexamethasone groups, respectively. The incidence of adverse reactions suggestive of heart failure (acute pulmonary edema, pulmonary edema, cardiac failure, congestive cardiac failure, cardiogenic shock) was ≤1% for each individual reaction in the VELCADE group. In the dexamethasone group the incidence was ≤1% for cardiac failure and congestive cardiac failure; there were no reported reactions of acute pulmonary edema, pulmonary edema, or cardiogenic shock. There have been isolated cases of QT-interval prolongation in clinical studies; causality has not been established.

5.4 Pulmonary Toxicity

Acute Respiratory Distress Syndrome (ARDS) and acute diffuse infiltrative pulmonary disease of unknown etiology such as pneumonitis, interstitial pneumonia, lung infiltration have occurred in patients receiving VELCADE. Some of these events have been fatal.

In a clinical trial, the first two patients given high-dose cytarabine (2 g/m^2 per day) by continuous infusion with daunorubicin and VELCADE for relapsed acute myelogenous leukemia died of ARDS early in the course of therapy.

There have been reports of pulmonary hypertension associated with VELCADE administration in the absence of left heart failure or significant pulmonary disease.

In the event of new or worsening cardiopulmonary symptoms, consider interrupting VELCADE until a prompt and comprehensive diagnostic evaluation is conducted.

5.5 Posterior Reversible Encephalopathy Syndrome (PRES)

Posterior Reversible Encephalopathy Syndrome (PRES; formerly termed Reversible Posterior Leukoencephalopathy Syndrome (RPLS)) has occurred in patients receiving VELCADE. PRES is a rare, reversible, neurological disorder which can present with seizure, hypertension, headache, lethargy, confusion, blindness, and other visual and neurological disturbances. Brain imaging, preferably MRI (Magnetic Resonance Imaging), is used to confirm the diagnosis. In patients developing PRES, discontinue VELCADE. The safety of reinitiating VELCADE therapy in patients previously experiencing PRES is not known.

5.6 Gastrointestinal Toxicity

VELCADE treatment can cause nausea, diarrhea, constipation, and vomiting [see Adverse Reactions (6.1)] sometimes requiring use of antiemetic and antidiarrheal medications. Ileus can occur. Fluid and electrolyte replacement should be administered to prevent dehydration. Interrupt VELCADE for severe symptoms.

5.7 Thrombocytopenia/Neutropenia

VELCADE is associated with thrombocytopenia and neutropenia that follow a cyclical pattern with nadirs occurring following the last dose of each cycle and typically recovering prior to initiation of the subsequent cycle. The cyclical pattern of platelet and neutrophil decreases and recovery remain consistent in the studies of multiple myeloma and mantle cell lymphoma, with no evidence of cumulative thrombocytopenia or neutropenia in the treatment regimens studied.

Monitor complete blood counts (CBC) frequently during treatment with VELCADE. Measure platelet counts prior to each dose of VELCADE. Adjust dose/schedule for thrombocytopenia [see Dosage and Administration (2.6)]. Gastrointestinal and intracerebral hemorrhage has occurred during thrombocytopenia in association with VELCADE. Support with transfusions and supportive care, according to published guidelines.

In the single agent, relapsed multiple myeloma study of VELCADE vs dexamethasone, the mean platelet count nadir measured was approximately 40% of baseline. The severity of thrombocytopenia related to pretreatment platelet count is shown in Table 8. The incidence of bleeding (≥Grade 3) was 2% on the VELCADE arm and was <1% in the dexamethasone arm.

Table 8: Severity of Thrombocytopenia Related to Pretreatment Platelet Count in the Relapsed Multiple Myeloma Study of VELCADE vs Dexamethasone
Pretreatment Platelet Count [A baseline platelet count of 50,000/µL was required for study eligibility] | Number of Patients (N=331) [Data were missing at baseline for one patient] | Number (%) of Patients with Platelet Count <10,000/µL | Number (%) of Patients with Platelet Count 10,000 to 25,000/µL
≥75,000/µL | 309 | 8 (3%) | 36 (12%)
≥50,000/µL to <75,000/µL | 14 | 2 (14%) | 11 (79%)
≥10,000/µL to <50,000/µL | 7 | 1 (14%) | 5 (71%)

In the combination study of VELCADE with rituximab, cyclophosphamide, doxorubicin and prednisone (VcR-CAP) in previously untreated mantle cell lymphoma patients, the incidence of thrombocytopenia (≥Grade 4) was 32% vs 1% for the rituximab, cyclophosphamide, doxorubicin, vincristine, and prednisone (R-CHOP) arm as shown in Table 12. The incidence of bleeding events (≥Grade 3) was 1.7% in the VcR-CAP arm (four patients) and was 1.2% in the R-CHOP arm (three patients).

Platelet transfusions were given to 23% of the patients in the VcR-CAP arm and 3% of the patients in the R-CHOP arm.

The incidence of neutropenia (≥Grade 4) was 70% in the VcR-CAP arm and was 52% in the R-CHOP arm. The incidence of febrile neutropenia (≥Grade 4) was 5% in the VcR-CAP arm and was 6% in the R-CHOP arm. Myeloid growth factor support was provided at a rate of 78% in the VcR-CAP arm and 61% in the R-CHOP arm.

5.8 Tumor Lysis Syndrome

Tumor lysis syndrome has been reported with VELCADE therapy. Patients at risk of tumor lysis syndrome are those with high tumor burden prior to treatment. Monitor patients closely and take appropriate precautions.

5.9 Hepatic Toxicity

Cases of acute liver failure have been reported in patients receiving multiple concomitant medications and with serious underlying medical conditions. Other reported hepatic reactions include hepatitis, increases in liver enzymes, and hyperbilirubinemia. Interrupt VELCADE therapy to assess reversibility. There is limited rechallenge information in these patients.

5.10 Thrombotic Microangiopathy

Cases, sometimes fatal, of thrombotic microangiopathy, including thrombotic thrombocytopenic purpura/hemolytic uremic syndrome (TTP/HUS), have been reported in the postmarketing setting in patients who received VELCADE. Monitor for signs and symptoms of TTP/HUS. If the diagnosis is suspected, stop VELCADE and evaluate. If the diagnosis of TTP/HUS is excluded, consider restarting VELCADE. The safety of reinitiating VELCADE therapy in patients previously experiencing TTP/HUS is not known.

5.11 Embryo-Fetal Toxicity

Based on the mechanism of action and findings in animals, VELCADE can cause fetal harm when administered to a pregnant woman. Bortezomib administered to rabbits during organogenesis at a dose approximately 0.5 times the clinical dose of 1.3 mg/m^2 based on body surface area caused postimplantation loss and a decreased number of live fetuses [see Use in Specific Populations (8.1)].

Advise females of reproductive potential to use effective contraception during treatment with VELCADE and for seven months following treatment. Advise males with female partners of reproductive potential to use effective contraception during treatment with VELCADE and for four months following treatment. If VELCADE is used during pregnancy or if the patient becomes pregnant during VELCADE treatment, the patient should be apprised of the potential risk to the fetus [see Use in Specific Populations (8.1, 8.3), Nonclinical Toxicology (13.1)].

6 ADVERSE REACTIONS

The following clinically significant adverse reactions are also discussed in other sections of the labeling:

- Peripheral Neuropathy [see Warnings and Precautions (5.1)]
- Hypotension [see Warnings and Precautions (5.2)]
- Cardiac Toxicity [see Warnings and Precautions (5.3)]
- Pulmonary Toxicity [see Warnings and Precautions (5.4)]
- Posterior Reversible Encephalopathy Syndrome (PRES) [see Warnings and Precautions (5.5)]
- Gastrointestinal Toxicity [see Warnings and Precautions (5.6)]
- Thrombocytopenia/Neutropenia [see Warnings and Precautions (5.7)]
- Tumor Lysis Syndrome [see Warnings and Precautions (5.8)]
- Hepatic Toxicity [see Warnings and Precautions (5.9)]
- Thrombotic Microangiopathy [see Warnings and Precautions (5.10)]

6.1 Clinical Trials Experience

Because clinical trials are conducted under widely varying conditions, adverse reaction rates observed in the clinical trials of a drug cannot be directly compared to rates in the clinical trials of another drug and may not reflect the rates observed in clinical practice.

Summary of Clinical Trial in Patients with Previously Untreated Multiple Myeloma

Table 9 describes safety data from 340 patients with previously untreated multiple myeloma who received VELCADE (1.3 mg/m^2) administered intravenously in combination with melphalan (9 mg/m^2) and prednisone (60 mg/m^2) in a prospective randomized study.

The safety profile of VELCADE in combination with melphalan/prednisone is consistent with the known safety profiles of both VELCADE and melphalan/prednisone.

Table 9: Most Commonly Reported Adverse Reactions (≥10% in the VELCADE, Melphalan and Prednisone Arm) with Grades 3 and ≥4 Intensity in the Previously Untreated Multiple Myeloma Study
 | VELCADE, Melphalan and Prednisone |  |  | Melphalan and Prednisone
 | (n=340) |  |  | (n=337)
Body System | Total | Toxicity Grade, n (%) |  | Total | Toxicity Grade, n (%)
Adverse Reaction | n (%) | 3 | ≥4 | n (%) | 3 | ≥4
Blood and Lymphatic System Disorders
Thrombocytopenia | 164 (48) | 60 (18) | 57 (17) | 140 (42) | 48 (14) | 39 (12)
Neutropenia | 160 (47) | 101 (30) | 33 (10) | 143 (42) | 77 (23) | 42 (12)
Anemia | 109 (32) | 41 (12) | 4 (1) | 156 (46) | 61 (18) | 18 (5)
Leukopenia | 108 (32) | 64 (19) | 8 (2) | 93 (28) | 53 (16) | 11 (3)
Lymphopenia | 78 (23) | 46 (14) | 17 (5) | 51 (15) | 26 (8) | 7 (2)
Gastrointestinal Disorders
Nausea | 134 (39) | 10 (3) | 0 | 70 (21) | 1 (<1) | 0
Diarrhea | 119 (35) | 19 (6) | 2 (1) | 20 (6) | 1 (<1) | 0
Vomiting | 87 (26) | 13 (4) | 0 | 41 (12) | 2 (1) | 0
Constipation | 77 (23) | 2 (1) | 0 | 14 (4) | 0 | 0
Abdominal pain upper | 34 (10) | 1 (<1) | 0 | 20 (6) | 0 | 0
Nervous System Disorders
Peripheral neuropathy [Represents High Level Term Peripheral Neuropathies NEC] | 156 (46) | 42 (12) | 2 (1) | 4 (1) | 0 | 0
Neuralgia | 117 (34) | 27 (8) | 2 (1) | 1 (<1) | 0 | 0
Paresthesia | 42 (12) | 6 (2) | 0 | 4 (1) | 0 | 0
General Disorders and Administration Site Conditions
Fatigue | 85 (25) | 19 (6) | 2 (1) | 48 (14) | 4 (1) | 0
Asthenia | 54 (16) | 18 (5) | 0 | 23 (7) | 3 (1) | 0
Pyrexia | 53 (16) | 4 (1) | 0 | 19 (6) | 1 (<1) | 1 (<1)
Infections and Infestations
Herpes Zoster | 39 (11) | 11 (3) | 0 | 9 (3) | 4 (1) | 0
Metabolism and Nutrition Disorders
Anorexia | 64 (19) | 6 (2) | 0 | 19 (6) | 0 | 0
Skin and Subcutaneous Tissue Disorders
Rash | 38 (11) | 2 (1) | 0 | 7 (2) | 0 | 0
Psychiatric Disorders
Insomnia | 35 (10) | 1 (<1) | 0 | 21 (6) | 0 | 0

Relapsed Multiple Myeloma Randomized Study of VELCADE vs Dexamethasone

The safety data described below and in Table 10 reflect exposure to either VELCADE (n=331) or dexamethasone (n=332) in a study of patients with relapsed multiple myeloma. VELCADE was administered intravenously at doses of 1.3 mg/m^2 twice weekly for two out of three weeks (21 day cycle). After eight, 21 day cycles patients continued therapy for three, 35 day cycles on a weekly schedule. Duration of treatment was up to 11 cycles (nine months) with a median duration of six cycles (4.1 months). For inclusion in the trial, patients must have had measurable disease and one to three prior therapies. There was no upper age limit for entry. Creatinine clearance could be as low as 20 mL/min and bilirubin levels as high as 1.5 times the upper limit of normal. The overall frequency of adverse reactions was similar in men and women, and in patients <65 and ≥65 years of age. Most patients were Caucasian [see Clinical Studies (14.1)].

Among the 331 VELCADE-treated patients, the most commonly reported (>20%) adverse reactions overall were nausea (52%), diarrhea (52%), fatigue (39%), peripheral neuropathies (35%), thrombocytopenia (33%), constipation (30%), vomiting (29%), and anorexia (21%). The most commonly reported (>20%) adverse reaction reported among the 332 patients in the dexamethasone group was fatigue (25%). Eight percent (8%) of patients in the VELCADE-treated arm experienced a Grade 4 adverse reaction; the most common reactions were thrombocytopenia (4%) and neutropenia (2%). Nine percent (9%) of dexamethasone-treated patients experienced a Grade 4 adverse reaction. All individual dexamethasone-related Grade 4 adverse reactions were less than 1%.

Serious Adverse Reactions and Adverse Reactions Leading to Treatment Discontinuation in the Relapsed Multiple Myeloma Study of VELCADE vs Dexamethasone

Serious adverse reactions are defined as any reaction that results in death, is life-threatening, requires hospitalization or prolongs a current hospitalization, results in a significant disability, or is deemed to be an important medical event. A total of 80 (24%) patients from the VELCADE treatment arm experienced a serious adverse reaction during the study, as did 83 (25%) dexamethasone-treated patients. The most commonly reported serious adverse reactions in the VELCADE treatment arm were diarrhea (3%), dehydration, herpes zoster, pyrexia, nausea, vomiting, dyspnea, and thrombocytopenia (2% each). In the dexamethasone treatment group, the most commonly reported serious adverse reactions were pneumonia (4%), hyperglycemia (3%), pyrexia, and psychotic disorder (2% each).

A total of 145 patients, including 84 (25%) of 331 patients in the VELCADE treatment group and 61 (18%) of 332 patients in the dexamethasone treatment group were discontinued from treatment due to adverse reactions. Among the 331 VELCADE-treated patients, the most commonly reported adverse reaction leading to discontinuation was peripheral neuropathy (8%). Among the 332 patients in the dexamethasone group, the most commonly reported adverse reactions leading to treatment discontinuation were psychotic disorder and hyperglycemia (2% each).

Four deaths were considered to be VELCADE-related in this relapsed multiple myeloma study: one case each of cardiogenic shock, respiratory insufficiency, congestive heart failure and cardiac arrest. Four deaths were considered dexamethasone-related: two cases of sepsis, one case of bacterial meningitis, and one case of sudden death at home.

Most Commonly Reported Adverse Reactions in the Relapsed Multiple Myeloma Study of VELCADE vs Dexamethasone

The most common adverse reactions from the relapsed multiple myeloma study are shown in Table 10. All adverse reactions with incidence ≥10% in the VELCADE arm are included.

Table 10: Most Commonly Reported Adverse Reactions (≥10% in VELCADE Arm), with Grades 3 and 4 Intensity in the Relapsed Multiple Myeloma Study of VELCADE vs Dexamethasone (N=663)
 | VELCADE (N=331) |  |  | Dexamethasone (N=332)
Adverse Reactions | All | Grade 3 | Grade 4 | All | Grade 3 | Grade 4
Any Adverse Reactions | 324 (98) | 193 (58) | 28 (8) | 297 (89) | 110 (33) | 29 (9)
Nausea | 172 (52) | 8 (2) | 0 | 31 (9) | 0 | 0
Diarrhea NOS | 171 (52) | 22 (7) | 0 | 36 (11) | 2 (<1) | 0
Fatigue | 130 (39) | 15 (5) | 0 | 82 (25) | 8 (2) | 0
Peripheral neuropathies [Represents High Level Term Peripheral Neuropathies NEC] | 115 (35) | 23 (7) | 2 (<1) | 14 (4) | 0 | 1 (<1)
Thrombocytopenia | 109 (33) | 80 (24) | 12 (4) | 11 (3) | 5 (2) | 1 (<1)
Constipation | 99 (30) | 6 (2) | 0 | 27 (8) | 1 (<1) | 0
Vomiting NOS | 96 (29) | 8 (2) | 0 | 10 (3) | 1 (<1) | 0
Anorexia | 68 (21) | 8 (2) | 0 | 8 (2) | 1 (<1) | 0
Pyrexia | 66 (20) | 2 (<1) | 0 | 21 (6) | 3 (<1) | 1 (<1)
Paresthesia | 64 (19) | 5 (2) | 0 | 24 (7) | 0 | 0
Anemia NOS | 63 (19) | 20 (6) | 1 (<1) | 21 (6) | 8 (2) | 0
Headache NOS | 62 (19) | 3 (<1) | 0 | 23 (7) | 1 (<1) | 0
Neutropenia | 58 (18) | 37 (11) | 8 (2) | 1 (<1) | 1 (<1) | 0
Rash NOS | 43 (13) | 3 (<1) | 0 | 7 (2) | 0 | 0
Appetite decreased NOS | 36 (11) | 0 | 0 | 12 (4) | 0 | 0
Dyspnea NOS | 35 (11) | 11 (3) | 1 (<1) | 37 (11) | 7 (2) | 1 (<1)
Abdominal pain NOS | 35 (11) | 5 (2) | 0 | 7 (2) | 0 | 0
Weakness | 34 (10) | 10 (3) | 0 | 28 (8) | 8 (2) | 0

Safety Experience from the Phase 2 Open-Label Extension Study in Relapsed Multiple Myeloma

In the Phase 2 extension study of 63 patients, no new cumulative or new long-term toxicities were observed with prolonged VELCADE treatment. These patients were treated for a total of 5.3 to 23 months, including time on VELCADE in the prior VELCADE study [see Clinical Studies (14.1)].

Safety Experience from the Phase 3 Open-Label Study of VELCADE Subcutaneous vs Intravenous in Relapsed Multiple Myeloma

The safety and efficacy of VELCADE administered subcutaneously were evaluated in one Phase 3 study at the recommended dose of 1.3 mg/m^2. This was a randomized, comparative study of VELCADE subcutaneous vs intravenous in 222 patients with relapsed multiple myeloma. The safety data described below and in Table 11 reflect exposure to either VELCADE subcutaneous (N=147) or VELCADE intravenous (N=74) [see Clinical Studies (14.1)].

Table 11: Most Commonly Reported Adverse Reactions (≥10%), with Grade 3 and ≥4 Intensity in the Relapsed Multiple Myeloma Study (N=221) of VELCADE Subcutaneous vs Intravenous
 | Subcutaneous |  |  | Intravenous
 | (N=147) |  |  | (N=74)
Body System | Total | Toxicity Grade, n (%) |  | Total | Toxicity Grade, n (%)
Adverse Reaction | n (%) | 3 | ≥4 | n (%) | 3 | ≥4
Blood and Lymphatic System Disorders
Anemia | 28 (19) | 8 (5) | 0 | 17 (23) | 3 (4) | 0
Leukopenia | 26 (18) | 8 (5) | 0 | 15 (20) | 4 (5) | 1 (1)
Neutropenia | 34 (23) | 15 (10) | 4 (3) | 20 (27) | 10 (14) | 3 (4)
Thrombocytopenia | 44 (30) | 7 (5) | 5 (3) | 25 (34) | 7 (9) | 5 (7)
Gastrointestinal Disorders
Diarrhea | 28 (19) | 1 (1) | 0 | 21 (28) | 3 (4) | 0
Nausea | 24 (16) | 0 | 0 | 10 (14) | 0 | 0
Vomiting | 13 (9) | 3 (2) | 0 | 8 (11) | 0 | 0
General Disorders and Administration Site Conditions
Asthenia | 10 (7) | 1 (1) | 0 | 12 (16) | 4 (5) | 0
Fatigue | 11 (7) | 3 (2) | 0 | 11 (15) | 3 (4) | 0
Pyrexia | 18 (12) | 0 | 0 | 6 (8) | 0 | 0
Nervous System Disorders
Neuralgia | 34 (23) | 5 (3) | 0 | 17 (23) | 7 (9) | 0
Peripheral neuropathies [Represents High Level Term Peripheral Neuropathies NEC] | 55 (37) | 8 (5) | 1 (1) | 37 (50) | 10 (14) | 1 (1)
Note: Safety population: 147 patients in the subcutaneous treatment group and 74 patients in the intravenous treatment group who received at least one dose of study medication

In general, safety data were similar for the subcutaneous and intravenous treatment groups. Differences were observed in the rates of some Grade ≥3 adverse reactions. Differences of ≥5% were reported in neuralgia (3% subcutaneous vs 9% intravenous), peripheral neuropathies (6% subcutaneous vs 15% intravenous), neutropenia (13% subcutaneous vs 18% intravenous), and thrombocytopenia (8% subcutaneous vs 16% intravenous).

A local reaction was reported in 6% of patients in the subcutaneous group, mostly redness. Only two (1%) patients were reported as having severe reactions, one case of pruritus and one case of redness. Local reactions led to reduction in injection concentration in one patient and drug discontinuation in one patient. Local reactions resolved in a median of six days.

Dose reductions occurred due to adverse reactions in 31% of patients in the subcutaneous treatment group compared with 43% of the intravenously-treated patients. The most common adverse reactions leading to a dose reduction included peripheral sensory neuropathy (17% in the subcutaneous treatment group compared with 31% in the intravenous treatment group); and neuralgia (11% in the subcutaneous treatment group compared with 19% in the intravenous treatment group).

Serious Adverse Reactions and Adverse Reactions Leading to Treatment Discontinuation in the Relapsed Multiple Myeloma Study of VELCADE Subcutaneous vs Intravenous

The incidence of serious adverse reactions was similar for the subcutaneous treatment group (20%) and the intravenous treatment group (19%). The most commonly reported serious adverse reactions in the subcutaneous treatment arm were pneumonia and pyrexia (2% each). In the intravenous treatment group, the most commonly reported serious adverse reactions were pneumonia, diarrhea, and peripheral sensory neuropathy (3% each).

In the subcutaneous treatment group, 27 patients (18%) discontinued study treatment due to an adverse reaction compared with 17 patients (23%) in the intravenous treatment group. Among the 147 subcutaneously-treated patients, the most commonly reported adverse reactions leading to discontinuation were peripheral sensory neuropathy (5%) and neuralgia (5%). Among the 74 patients in the intravenous treatment group, the most commonly reported adverse reactions leading to treatment discontinuation were peripheral sensory neuropathy (9%) and neuralgia (9%).

Two patients (1%) in the subcutaneous treatment group and one (1%) patient in the intravenous treatment group died due to an adverse reaction during treatment. In the subcutaneous group the causes of death were one case of pneumonia and one case of sudden death. In the intravenous group the cause of death was coronary artery insufficiency.

Safety Experience from the Clinical Trial in Patients with Previously Untreated Mantle Cell Lymphoma

Table 12 describes safety data from 240 patients with previously untreated mantle cell lymphoma who received VELCADE (1.3 mg/m^2) administered intravenously in combination with rituximab (375 mg/m^2), cyclophosphamide (750 mg/m^2), doxorubicin (50 mg/m^2), and prednisone (100 mg/m^2) (VcR-CAP) in a prospective randomized study.

Infections were reported for 31% of patients in the VcR-CAP arm and 23% of the patients in the comparator (rituximab, cyclophosphamide, doxorubicin, vincristine, and prednisone [R-CHOP]) arm, including the predominant preferred term of pneumonia (VcR-CAP 8% vs R-CHOP 5%).

Table 12: Most Commonly Reported Adverse Reactions (≥5%) with Grades 3 and ≥4 Intensity in the Previously Untreated Mantle Cell Lymphoma Study
 | VcR-CAP (n=240) |  |  | R-CHOP (n=242)
Body System Adverse Reactions | All n (%) | Toxicity Grade 3 n (%) | Toxicity Grade ≥4 n (%) | All n (%) | Toxicity Grade 3 n (%) | Toxicity Grade ≥4 n (%)
Key: R-CHOP = rituximab, cyclophosphamide, doxorubicin, vincristine, and prednisone; VcR-CAP = VELCADE, rituximab, cyclophosphamide, doxorubicin, and prednisone.
Blood and Lymphatic System Disorders
Neutropenia | 209 (87) | 32 (13) | 168 (70) | 172 (71) | 31 (13) | 125 (52)
Leukopenia | 116 (48) | 34 (14) | 69 (29) | 87 (36) | 39 (16) | 27 (11)
Anemia | 106 (44) | 27 (11) | 4 (2) | 71 (29) | 23 (10) | 4 (2)
Thrombocytopenia | 172 (72) | 59 (25) | 76 (32) | 42 (17) | 9 (4) | 3 (1)
Febrile neutropenia | 41 (17) | 24 (10) | 12 (5) | 33 (14) | 17 (7) | 15 (6)
Lymphopenia | 68 (28) | 25 (10) | 36 (15) | 28 (12) | 15 (6) | 2 (1)
Nervous System Disorders
Peripheral neuropathy [Represents High Level Term Peripheral Neuropathies NEC] | 71 (30) | 17 (7) | 1 (<1) | 65 (27) | 10 (4) | 0
Hypoesthesia | 14 (6) | 3 (1) | 0 | 13 (5) | 0 | 0
Paresthesia | 14 (6) | 2 (1) | 0 | 11 (5) | 0 | 0
Neuralgia | 25 (10) | 9 (4) | 0 | 1 (<1) | 0 | 0
General Disorders and Administration Site Conditions
Fatigue | 43 (18) | 11 (5) | 1 (<1) | 38 (16) | 5 (2) | 0
Pyrexia | 48 (20) | 7 (3) | 0 | 23 (10) | 5 (2) | 0
Asthenia | 29 (12) | 4 (2) | 1 (<1) | 18 (7) | 1 (<1) | 0
Edema peripheral | 16 (7) | 1 (<1) | 0 | 13 (5) | 0 | 0
Gastrointestinal Disorders
Nausea | 54 (23) | 1 (<1) | 0 | 28 (12) | 0 | 0
Constipation | 42 (18) | 1 (<1) | 0 | 22 (9) | 2 (1) | 0
Stomatitis | 20 (8) | 2 (1) | 0 | 19 (8) | 0 | 1 (<1)
Diarrhea | 59 (25) | 11 (5) | 0 | 11 (5) | 3 (1) | 1 (<1)
Vomiting | 24 (10) | 1 (<1) | 0 | 8 (3) | 0 | 0
Abdominal distension | 13 (5) | 0 | 0 | 4 (2) | 0 | 0
Infections and Infestations
Pneumonia | 20 (8) | 8 (3) | 5 (2) | 11 (5) | 5 (2) | 3 (1)
Skin and Subcutaneous Tissue Disorders
Alopecia | 31 (13) | 1 (<1) | 1 (<1) | 33 (14) | 4 (2) | 0
Metabolism and Nutrition Disorders
Hyperglycemia | 10 (4) | 1 (<1) | 0 | 17 (7) | 10 (4) | 0
Decreased appetite | 36 (15) | 2 (1) | 0 | 15 (6) | 1 (<1) | 0
Vascular Disorders
Hypertension | 15 (6) | 1 (<1) | 0 | 3 (1) | 0 | 0
Psychiatric Disorders
Insomnia | 16 (7) | 1 (<1) | 0 | 8 (3) | 0 | 0

The incidence of herpes zoster reactivation was 4.6% in the VcR-CAP arm and 0.8% in the R-CHOP arm. Antiviral prophylaxis was mandated by protocol amendment.

The incidences of Grade ≥3 bleeding events were similar between the two arms (four patients in the VcR-CAP arm and three patients in the R-CHOP arm). All of the Grade ≥3 bleeding events resolved without sequelae in the VcR-CAP arm.

Adverse reactions leading to discontinuation occurred in 8% of patients in VcR-CAP group and 6% of patients in R-CHOP group. In the VcR-CAP group, the most commonly reported adverse reaction leading to discontinuation was peripheral sensory neuropathy (1%; three patients). The most commonly reported adverse reaction leading to discontinuation in the R-CHOP group was febrile neutropenia (<1%; two patients).

Integrated Summary of Safety (Relapsed Multiple Myeloma and Relapsed Mantle Cell Lymphoma)

Safety data from Phase 2 and 3 studies of single agent VELCADE 1.3 mg/m^2/dose twice weekly for two weeks followed by a ten day rest period in 1163 patients with previously-treated multiple myeloma (N=1008) and previously-treated mantle cell lymphoma (N=155) were integrated and tabulated. This analysis does not include data from the Phase 3 open-label study of VELCADE subcutaneous vs intravenous in relapsed multiple myeloma. In the integrated studies, the safety profile of VELCADE was similar in patients with multiple myeloma and mantle cell lymphoma.

In the integrated analysis, the most commonly reported (>20%) adverse reactions were nausea (49%), diarrhea (46%), asthenic conditions including fatigue (41%) and weakness (11%), peripheral neuropathies (38%), thrombocytopenia (32%), vomiting (28%), constipation (25%), and pyrexia (21%). Eleven percent (11%) of patients experienced at least one episode of ≥Grade 4 toxicity, most commonly thrombocytopenia (4%) and neutropenia (2%).

In the Phase 2 relapsed multiple myeloma clinical trials of VELCADE administered intravenously, local skin irritation was reported in 5% of patients, but extravasation of VELCADE was not associated with tissue damage.

Serious Adverse Reactions and Adverse Reactions Leading to Treatment Discontinuation in the Integrated Summary of Safety

A total of 26% of patients experienced a serious adverse reaction during the studies. The most commonly reported serious adverse reactions included diarrhea, vomiting and pyrexia (3% each), nausea, dehydration, and thrombocytopenia (2% each) and pneumonia, dyspnea, peripheral neuropathies, and herpes zoster (1% each).

Adverse reactions leading to discontinuation occurred in 22% of patients. The reasons for discontinuation included peripheral neuropathy (8%), and fatigue, thrombocytopenia, and diarrhea (2% each).

In total, 2% of the patients died and the cause of death was considered by the investigator to be possibly related to study drug: including reports of cardiac arrest, congestive heart failure, respiratory failure, renal failure, pneumonia and sepsis.

Most Commonly Reported Adverse Reactions in the Integrated Summary of Safety

The most common adverse reactions are shown in Table 13. All adverse reactions occurring at ≥10% are included. In the absence of a randomized comparator arm, it is often not possible to distinguish between adverse events that are drug-caused and those that reflect the patient's underlying disease. Please see the discussion of specific adverse reactions that follows.

Table 13: Most Commonly Reported (≥10% Overall) Adverse Reactions in Integrated Analyses of Relapsed Multiple Myeloma and Relapsed Mantle Cell Lymphoma Studies Using the 1.3 mg/m^2 Dose (N=1163)
 | All Patients (N=1163) |  | Multiple Myeloma (N=1008) |  | Mantle Cell Lymphoma (N=155)
Adverse Reactions | All | ≥Grade 3 | All | ≥Grade 3 | All | ≥Grade 3
Nausea | 567 (49) | 36 (3) | 511 (51) | 32 (3) | 56 (36) | 4 (3)
Diarrhea NOS | 530 (46) | 83 (7) | 470 (47) | 72 (7) | 60 (39) | 11 (7)
Fatigue | 477 (41) | 86 (7) | 396 (39) | 71 (7) | 81 (52) | 15 (10)
Peripheral neuropathies [Represents High Level Term Peripheral Neuropathies NEC] | 443 (38) | 129 (11) | 359 (36) | 110 (11) | 84 (54) | 19 (12)
Thrombocytopenia | 369 (32) | 295 (25) | 344 (34) | 283 (28) | 25 (16) | 12 (8)
Vomiting NOS | 321 (28) | 44 (4) | 286 (28) | 40 (4) | 35 (23) | 4 (3)
Constipation | 296 (25) | 17 (1) | 244 (24) | 14 (1) | 52 (34) | 3 (2)
Pyrexia | 249 (21) | 16 (1) | 233 (23) | 15 (1) | 16 (10) | 1 (<1)
Anorexia | 227 (20) | 19 (2) | 205 (20) | 16 (2) | 22 (14) | 3 (2)
Anemia NOS | 209 (18) | 65 (6) | 190 (19) | 63 (6) | 19 (12) | 2 (1)
Headache NOS | 175 (15) | 8 (<1) | 160 (16) | 8 (<1) | 15 (10) | 0
Neutropenia | 172 (15) | 121 (10) | 164 (16) | 117 (12) | 8 (5) | 4 (3)
Rash NOS | 156 (13) | 8 (<1) | 120 (12) | 4 (<1) | 36 (23) | 4 (3)
Paresthesia | 147 (13) | 9 (<1) | 136 (13) | 8 (<1) | 11 (7) | 1 (<1)
Dizziness (excl vertigo) | 129 (11) | 13 (1) | 101 (10) | 9 (<1) | 28 (18) | 4 (3)
Weakness | 124 (11) | 31 (3) | 106 (11) | 28 (3) | 18 (12) | 3 (2)

Description of Selected Adverse Reactions from the Integrated Phase 2 and 3 Relapsed Multiple Myeloma and Phase 2 Relapsed Mantle Cell Lymphoma Studies

Gastrointestinal Toxicity

A total of 75% of patients experienced at least one gastrointestinal disorder. The most common gastrointestinal disorders included nausea, diarrhea, constipation, vomiting, and appetite decreased. Other gastrointestinal disorders included dyspepsia and dysgeusia. Grade 3 adverse reactions occurred in 14% of patients; ≥Grade 4 adverse reactions were ≤1%. Gastrointestinal adverse reactions were considered serious in 7% of patients. Four percent (4%) of patients discontinued due to a gastrointestinal adverse reaction. Nausea was reported more often in patients with multiple myeloma (51%) compared to patients with mantle cell lymphoma (36%).

Thrombocytopenia

Across the studies, VELCADE-associated thrombocytopenia was characterized by a decrease in platelet count during the dosing period (Days 1 to 11) and a return toward baseline during the ten day rest period during each treatment cycle. Overall, thrombocytopenia was reported in 32% of patients. Thrombocytopenia was Grade 3 in 22%, ≥Grade 4 in 4%, and serious in 2% of patients, and the reaction resulted in VELCADE discontinuation in 2% of patients [see Warnings and Precautions (5.7)]. Thrombocytopenia was reported more often in patients with multiple myeloma (34%) compared to patients with mantle cell lymphoma (16%). The incidence of ≥Grade 3 thrombocytopenia also was higher in patients with multiple myeloma (28%) compared to patients with mantle cell lymphoma (8%).

Peripheral Neuropathy

Overall, peripheral neuropathies occurred in 38% of patients. Peripheral neuropathy was Grade 3 for 11% of patients and ≥Grade 4 for <1% of patients. Eight percent (8%) of patients discontinued VELCADE due to peripheral neuropathy. The incidence of peripheral neuropathy was higher among patients with mantle cell lymphoma (54%) compared to patients with multiple myeloma (36%).

In the VELCADE vs dexamethasone Phase 3 relapsed multiple myeloma study, among the 62 VELCADE-treated patients who experienced ≥Grade 2 peripheral neuropathy and had dose adjustments, 48% had improved or resolved with a median of 3.8 months from first onset.

In the Phase 2 relapsed multiple myeloma studies, among the 30 patients who experienced Grade 2 peripheral neuropathy resulting in discontinuation or who experienced ≥Grade 3 peripheral neuropathy, 73% reported improvement or resolution with a median time of 47 days to improvement of one grade or more from the last dose of VELCADE.

Hypotension

The incidence of hypotension (postural, orthostatic and hypotension NOS) was 8% in patients treated with VELCADE. Hypotension was Grade 1 or 2 in the majority of patients and Grade 3 in 2% and ≥Grade 4 in <1%. Two percent (2%) of patients had hypotension reported as a serious adverse reaction, and 1% discontinued due to hypotension. The incidence of hypotension was similar in patients with multiple myeloma (8%) and those with mantle cell lymphoma (9%). In addition, <1% of patients experienced hypotension associated with a syncopal reaction.

Neutropenia

Neutrophil counts decreased during the VELCADE dosing period (Days 1 to 11) and returned toward baseline during the ten day rest period during each treatment cycle. Overall, neutropenia occurred in 15% of patients and was Grade 3 in 8% of patients and ≥Grade 4 in 2%. Neutropenia was reported as a serious adverse reaction in <1% of patients and <1% of patients discontinued due to neutropenia. The incidence of neutropenia was higher in patients with multiple myeloma (16%) compared to patients with mantle cell lymphoma (5%). The incidence of ≥Grade 3 neutropenia also was higher in patients with multiple myeloma (12%) compared to patients with mantle cell lymphoma (3%).

Asthenic Conditions (Fatigue, Malaise, Weakness, Asthenia)

Asthenic conditions were reported in 54% of patients. Fatigue was reported as Grade 3 in 7% and ≥Grade 4 in <1% of patients. Asthenia was reported as Grade 3 in 2% and ≥Grade 4 in <1% of patients. Two percent (2%) of patients discontinued treatment due to fatigue and <1% due to weakness and asthenia. Asthenic conditions were reported in 53% of patients with multiple myeloma and 59% of patients with mantle cell lymphoma.

Pyrexia

Pyrexia (>38°C) was reported as an adverse reaction for 21% of patients. The reaction was Grade 3 in 1% and ≥Grade 4 in <1%. Pyrexia was reported as a serious adverse reaction in 3% of patients and led to VELCADE discontinuation in <1% of patients. The incidence of pyrexia was higher among patients with multiple myeloma (23%) compared to patients with mantle cell lymphoma (10%). The incidence of ≥Grade 3 pyrexia was 1% in patients with multiple myeloma and <1% in patients with mantle cell lymphoma.

Herpes Virus Infection

Consider using antiviral prophylaxis in subjects being treated with VELCADE. In the randomized studies in previously untreated and relapsed multiple myeloma, herpes zoster reactivation was more common in subjects treated with VELCADE (ranging between 6 to 11%) than in the control groups (3 to 4%). Herpes simplex was seen in 1 to 3% in subjects treated with VELCADE and 1 to 3% in the control groups. In the previously untreated multiple myeloma study, herpes zoster virus reactivation in the VELCADE, melphalan and prednisone arm was less common in subjects receiving prophylactic antiviral therapy (3%) than in subjects who did not receive prophylactic antiviral therapy (17%).

Retreatment in Relapsed Multiple Myeloma

A single-arm trial was conducted in 130 patients with relapsed multiple myeloma to determine the efficacy and safety of retreatment with intravenous VELCADE. The safety profile of patients in this trial is consistent with the known safety profile of VELCADE-treated patients with relapsed multiple myeloma as demonstrated in Tables 10, 11, and 13; no cumulative toxicities were observed upon retreatment. The most common adverse drug reaction was thrombocytopenia which occurred in 52% of the patients. The incidence of ≥Grade 3 thrombocytopenia was 24%. Peripheral neuropathy occurred in 28% of patients, with the incidence of ≥Grade 3 peripheral neuropathy reported at 6%. The incidence of serious adverse reactions was 12.3%. The most commonly reported serious adverse reactions were thrombocytopenia (3.8%), diarrhea (2.3%), and herpes zoster and pneumonia (1.5% each).

Adverse reactions leading to discontinuation occurred in 13% of patients. The reasons for discontinuation included peripheral neuropathy (5%) and diarrhea (3%).

Two deaths considered to be VELCADE-related occurred within 30 days of the last VELCADE dose; one in a patient with cerebrovascular accident and one in a patient with sepsis.

Additional Adverse Reactions from Clinical Studies

The following clinically important serious adverse reactions that are not described above have been reported in clinical trials in patients treated with VELCADE administered as monotherapy or in combination with other chemotherapeutics. These studies were conducted in patients with hematological malignancies and in solid tumors.

Blood and Lymphatic System Disorders: Anemia, disseminated intravascular coagulation, febrile neutropenia, lymphopenia, leukopenia

Cardiac Disorders: Angina pectoris, atrial fibrillation aggravated, atrial flutter, bradycardia, sinus arrest, cardiac amyloidosis, complete atrioventricular block, myocardial ischemia, myocardial infarction, pericarditis, pericardial effusion, Torsades de pointes, ventricular tachycardia

Ear and Labyrinth Disorders: Hearing impaired, vertigo

Eye Disorders: Diplopia and blurred vision, conjunctival infection, irritation

Gastrointestinal Disorders: Abdominal pain, ascites, dysphagia, fecal impaction, gastroenteritis, gastritis hemorrhagic, hematemesis, hemorrhagic duodenitis, ileus paralytic, large intestinal obstruction, paralytic intestinal obstruction, peritonitis, small intestinal obstruction, large intestinal perforation, stomatitis, melena, pancreatitis acute, oral mucosal petechiae, gastroesophageal reflux

General Disorders and Administration Site Conditions: Chills, edema, edema peripheral, injection site erythema, neuralgia, injection site pain, irritation, malaise, phlebitis

Hepatobiliary Disorders: Cholestasis, hepatic hemorrhage, hyperbilirubinemia, portal vein thrombosis, hepatitis, liver failure

Immune System Disorders: Anaphylactic reaction, drug hypersensitivity, immune complex mediated hypersensitivity, angioedema, laryngeal edema

Infections and Infestations: Aspergillosis, bacteremia, bronchitis, urinary tract infection, herpes viral infection, listeriosis, nasopharyngitis, pneumonia, respiratory tract infection, septic shock, toxoplasmosis, oral candidiasis, sinusitis, catheter-related infection

Injury, Poisoning and Procedural Complications: Catheter-related complication, skeletal fracture, subdural hematoma

Investigations: Weight decreased

Metabolism and Nutrition Disorders: Dehydration, hypocalcemia, hyperuricemia, hypokalemia, hyperkalemia, hyponatremia, hypernatremia

Musculoskeletal and Connective Tissue Disorders: Arthralgia, back pain, bone pain, myalgia, pain in extremity

Nervous System Disorders: Ataxia, coma, dizziness, dysarthria, dysesthesia, dysautonomia, encephalopathy, cranial palsy, grand mal convulsion, headache, hemorrhagic stroke, motor dysfunction, neuralgia, spinal cord compression, paralysis, postherpetic neuralgia, transient ischemic attack

Psychiatric Disorders: Agitation, anxiety, confusion, insomnia, mental status change, psychotic disorder, suicidal ideation

Renal and Urinary Disorders: Calculus renal, bilateral hydronephrosis, bladder spasm, hematuria, hemorrhagic cystitis, urinary incontinence, urinary retention, renal failure (acute and chronic), glomerular nephritis proliferative

Respiratory, Thoracic and Mediastinal Disorders: Acute respiratory distress syndrome, aspiration pneumonia, atelectasis, chronic obstructive airways disease exacerbated, cough, dysphagia, dyspnea, dyspnea exertional, epistaxis, hemoptysis, hypoxia, lung infiltration, pleural effusion, pneumonitis, respiratory distress, pulmonary hypertension

Skin and Subcutaneous Tissue Disorders: Urticaria, face edema, rash (which may be pruritic), leukocytoclastic vasculitis, pruritus

Vascular Disorders: Cerebrovascular accident, cerebral hemorrhage, deep venous thrombosis, hypertension, peripheral embolism, pulmonary embolism, pulmonary hypertension

6.2 Postmarketing Experience

The following adverse reactions have been identified from the worldwide postmarketing experience with VELCADE. Because these reactions are reported voluntarily from a population of uncertain size, it is not always possible to reliably estimate their frequency or establish a causal relationship to drug exposure:

Cardiac Disorders: Cardiac tamponade

Ear and Labyrinth Disorders: Deafness bilateral

Eye Disorders: Optic neuropathy, blindness, chalazion/blepharitis

Gastrointestinal Disorders: Ischemic colitis

Infections and Infestations: Progressive multifocal leukoencephalopathy (PML), ophthalmic herpes, herpes meningoencephalitis

Nervous System Disorders: Posterior reversible encephalopathy syndrome (PRES, formerly RPLS), Guillain-Barré syndrome, demyelinating polyneuropathy

Respiratory, Thoracic and Mediastinal Disorders: Acute diffuse infiltrative pulmonary disease

Skin and Subcutaneous Tissue Disorders: Stevens-Johnson syndrome/toxic epidermal necrolysis (SJS/TEN), acute febrile neutrophilic dermatosis (Sweet's syndrome)

7 DRUG INTERACTIONS

7.1 Effects of Other Drugs on VELCADE

Strong CYP3A4 Inducers

Coadministration with a strong CYP3A4 inducer decreases the exposure of bortezomib [see Clinical Pharmacology (12.3)] which may decrease VELCADE efficacy. Avoid coadministration with strong CYP3A4 inducers.

Strong CYP3A4 Inhibitors

Coadministration with a strong CYP3A4 inhibitor increases the exposure of bortezomib [see Clinical Pharmacology (12.3)] which may increase the risk of VELCADE toxicities. Monitor patients for signs of bortezomib toxicity and consider a bortezomib dose reduction if bortezomib must be given in combination with strong CYP3A4 inhibitors.

7.2 Drugs Without Clinically Significant Interactions with VELCADE

No clinically significant drug interactions have been observed when VELCADE was coadministered with dexamethasone, omeprazole, or melphalan in combination with prednisone [see Clinical Pharmacology (12.3)].

8 USE IN SPECIFIC POPULATIONS

8.1 Pregnancy

Risk Summary

Based on its mechanism of action [see Clinical Pharmacology (12.1)] and findings in animals, VELCADE can cause fetal harm when administered to a pregnant woman. There are no studies with the use of VELCADE in pregnant women to inform drug-associated risks. Bortezomib caused embryo-fetal lethality in rabbits at doses lower than the clinical dose (see Data). Advise pregnant women of the potential risk to the fetus.

Adverse outcomes in pregnancy occur regardless of the health of the mother or the use of medications. The estimated background risk of major birth defects and miscarriage for the indicated population is unknown. In the U.S. general population, the estimated background risk of major birth defects and miscarriage in clinically recognized pregnancies is 2 to 4% and 15 to 20%, respectively.

Data

Animal Data

Bortezomib was not teratogenic in nonclinical developmental toxicity studies in rats and rabbits at the highest dose tested (0.075 mg/kg; 0.5 mg/m^2 in the rat and 0.05 mg/kg; 0.6 mg/m^2 in the rabbit) when administered during organogenesis. These dosages are approximately 0.5 times the clinical dose of 1.3 mg/m^2 based on body surface area.

Bortezomib caused embryo-fetal lethality in rabbits at doses lower than the clinical dose (approximately 0.5 times the clinical dose of 1.3 mg/m^2 based on body surface area). Pregnant rabbits given bortezomib during organogenesis at a dose of 0.05 mg/kg (0.6 mg/m^2) experienced significant postimplantation loss and decreased number of live fetuses. Live fetuses from these litters also showed significant decreases in fetal weight.

8.2 Lactation

Risk Summary

There are no data on the presence of bortezomib or its metabolites in human milk, the effects of the drug on the breastfed child, or the effects of the drug on milk production. Because many drugs are excreted in human milk and because the potential for serious adverse reactions in a breastfed child from VELCADE is unknown, advise nursing women not to breastfeed during treatment with VELCADE and for two months after treatment.

8.3 Females and Males of Reproductive Potential

Based on its mechanism of action and findings in animals, VELCADE can cause fetal harm when administered to a pregnant woman [see Use in Specific Populations (8.1)].

Pregnancy Testing

Conduct pregnancy testing in females of reproductive potential prior to initiating VELCADE treatment.

Contraception

Females

Advise females of reproductive potential to use effective contraception during treatment with VELCADE and for seven months after the last dose.

Males

Males with female partners of reproductive potential should use effective contraception during treatment with VELCADE and for four months after the last dose.

Infertility

Based on the mechanism of action and findings in animals, VELCADE may have an effect on either male or female fertility [see Nonclinical Toxicology (13.1)].

8.4 Pediatric Use

Safety and effectiveness have not been established in pediatric patients.

The activity and safety of VELCADE in combination with intensive reinduction chemotherapy was evaluated in pediatric and young adult patients with lymphoid malignancies (pre-B cell ALL 77%, 16% with T-cell ALL, and 7% T-cell lymphoblastic lymphoma (LL)), all of whom relapsed within 36 months of initial diagnosis in a single-arm multicenter, nonrandomized cooperative group trial. An effective reinduction multiagent chemotherapy regimen was administered in three blocks. Block 1 included vincristine, prednisone, doxorubicin and pegaspargase; Block 2 included cyclophosphamide, etoposide and methotrexate; Block 3 included high-dose cytosine arabinoside and asparaginase. VELCADE was administered at a dose of 1.3 mg/m^2 as a bolus intravenous injection on Days 1, 4, 8, and 11 of Block 1 and Days 1, 4, and 8 of Block 2. There were 140 patients with ALL or LL enrolled and evaluated for safety. The median age was ten years (range: 1 to 26), 57% were male, 70% were white, 14% were black, 4% were Asian, 2% were American Indian/Alaska Native, 1% were Pacific Islander.

The activity was evaluated in a prespecified subset of the first 60 evaluable patients enrolled on the study with pre-B ALL ≤21 years and relapsed <36 months from diagnosis. The complete remission (CR) rate at day 36 was compared to that in a historical control set of patients who had received the identical backbone therapy without VELCADE. There was no evidence that the addition of VELCADE had any impact on the CR rate.

No new safety concerns were observed when VELCADE was added to a chemotherapy backbone regimen as compared with a historical control group in which the backbone regimen was given without VELCADE.

The BSA-normalized clearance of bortezomib in pediatric patients was similar to that observed in adults.

8.5 Geriatric Use

Of the 669 patients enrolled in the relapsed multiple myeloma study, 245 (37%) were 65 years of age or older: 125 (38%) on the VELCADE arm and 120 (36%) on the dexamethasone arm. Median time to progression and median duration of response for patients ≥65 were longer on VELCADE compared to dexamethasone [5.5 mo vs 4.3 mo, and 8.0 mo vs 4.9 mo, respectively]. On the VELCADE arm, 40% (n=46) of evaluable patients aged ≥65 experienced response (CR + PR) vs 18% (n=21) on the dexamethasone arm. The incidence of Grade 3 and 4 events was 64%, 78% and 75% for VELCADE patients ≤50, 51 to 64 and ≥65 years old, respectively [see Adverse Reactions (6.1), Clinical Studies (14.1)].

No overall differences in safety or effectiveness were observed between patients ≥age 65 and younger patients receiving VELCADE; but greater sensitivity of some older individuals cannot be ruled out.

8.6 Renal Impairment

No starting dosage adjustment of VELCADE is recommended for patients with renal impairment. In patients requiring dialysis, VELCADE should be administered after the dialysis procedure [see Clinical Pharmacology (12.3)].

8.7 Hepatic Impairment

No starting dosage adjustment of VELCADE is recommended for patients with mild hepatic impairment (total bilirubin ≤1× ULN and AST >ULN, or total bilirubin >1 to 1.5× ULN and any AST). The exposure of bortezomib is increased in patients with moderate (total bilirubin ≥1.5 to 3× ULN and any AST) and severe (total bilirubin >3× ULN and any AST) hepatic impairment. Reduce the starting dose in patients with moderate or severe hepatic impairment [see Dosage and Administration (2.8), Clinical Pharmacology (12.3)].

8.8 Patients with Diabetes

During clinical trials, hypoglycemia and hyperglycemia were reported in diabetic patients receiving oral hypoglycemics. Patients on oral antidiabetic agents receiving VELCADE treatment may require close monitoring of their blood glucose levels and adjustment of the dose of their antidiabetic medication.

10 OVERDOSAGE

There is no known specific antidote for VELCADE overdosage. In humans, fatal outcomes following the administration of more than twice the recommended therapeutic dose have been reported, which were associated with the acute onset of symptomatic hypotension (5.2) and thrombocytopenia (5.7). In the event of an overdosage, the patient's vital signs should be monitored and appropriate supportive care given.

Studies in monkeys and dogs showed that intravenous bortezomib doses as low as two times the recommended clinical dose on a mg/m^2 basis were associated with increases in heart rate, decreases in contractility, hypotension, and death. In dog studies, a slight increase in the corrected QT interval was observed at doses resulting in death. In monkeys, doses of 3.0 mg/m^2 and greater (approximately twice the recommended clinical dose) resulted in hypotension starting at one hour postadministration, with progression to death in 12 to 14 hours following drug administration.

11 DESCRIPTION

VELCADE® for Injection, a proteasome inhibitor, contains bortezomib which is an antineoplastic agent. Bortezomib is a modified dipeptidyl boronic acid. The chemical name for bortezomib, the monomeric boronic acid, is [(1R)-3-methyl-1-[[(2S)-1-oxo-3-phenyl-2-[(pyrazinylcarbonyl) amino]propyl]amino]butyl] boronic acid.

Bortezomib has the following chemical structure:

The molecular weight is 384.24. The molecular formula is C19 H25 BN4 O4. The solubility of bortezomib, as the monomeric boronic acid, in water is 3.3 to 3.8 mg/mL in a pH range of 2 to 6.5.

VELCADE is available for intravenous injection or subcutaneous use. Each single-dose vial contains 3.5 mg of bortezomib as a sterile lyophilized powder. It also contains the inactive ingredient: 35 mg mannitol, USP. The product is provided as a mannitol boronic ester which, in reconstituted form, consists of the mannitol ester in equilibrium with its hydrolysis product, the monomeric boronic acid. The drug substance exists in its cyclic anhydride form as a trimeric boroxine.

12 CLINICAL PHARMACOLOGY

12.1 Mechanism of Action

Bortezomib is a reversible inhibitor of the chymotrypsin-like activity of the 26S proteasome in mammalian cells. The 26S proteasome is a large protein complex that degrades ubiquitinated proteins. The ubiquitin-proteasome pathway plays an essential role in regulating the intracellular concentration of specific proteins, thereby maintaining homeostasis within cells. Inhibition of the 26S proteasome prevents this targeted proteolysis, which can affect multiple signaling cascades within the cell. This disruption of normal homeostatic mechanisms can lead to cell death. Experiments have demonstrated that bortezomib is cytotoxic to a variety of cancer cell types in vitro. Bortezomib causes a delay in tumor growth in vivo in nonclinical tumor models, including multiple myeloma.

12.2 Pharmacodynamics

Following twice weekly administration of 1 mg/m^2 and 1.3 mg/m^2 bortezomib doses, the maximum inhibition of 20S proteasome activity (relative to baseline) in whole blood was observed five minutes after drug administration. Comparable maximum inhibition of 20S proteasome activity was observed between 1 and 1.3 mg/m^2 doses. Maximal inhibition ranged from 70% to 84% and from 73% to 83% for the 1 mg/m^2 and 1.3 mg/m^2 dose regimens, respectively.

12.3 Pharmacokinetics

Following intravenous administration of 1 mg/m^2 and 1.3 mg/m^2 doses, the mean maximum plasma concentrations of bortezomib (Cmax) after the first dose (Day 1) were 57 and 112 ng/mL, respectively. When administered twice weekly, the mean maximum observed plasma concentrations ranged from 67 to 106 ng/mL for the 1 mg/m^2 dose and 89 to 120 ng/mL for the 1.3 mg/m^2 dose.

Following an intravenous bolus or subcutaneous injection of a 1.3 mg/m^2 dose to patients with multiple myeloma, the total systemic exposure after repeat dose administration (AUClast) was equivalent for subcutaneous and intravenous administration. The AUClast geometric mean ratio (90% confidence interval) was 0.99 (0.80 to 1.23). The Cmax after subcutaneous administration (20.4 ng/mL) was lower than after intravenous administration (223 ng/mL) with repeat dose administration.

Distribution

The mean distribution volume of bortezomib ranged from approximately 498 to 1884 L/m^2 following single- or repeat-dose administration of 1 mg/m^2 or 1.3 mg/m^2 to patients with multiple myeloma. The binding of bortezomib to human plasma proteins averaged 83% over the concentration range of 100 to 1000 ng/mL.

Elimination

The mean elimination half-life of bortezomib upon multiple dosing ranged from 40 to 193 hours after the 1 mg/m^2 dose and 76 to 108 hours after the 1.3 mg/m^2 dose. The mean total body clearances were 102 and 112 L/h following the first dose for doses of 1 mg/m^2 and 1.3 mg/m^2, respectively, and ranged from 15 to 32 L/h following subsequent doses for doses of 1 and 1.3 mg/m^2, respectively.

Metabolism

Bortezomib is primarily oxidatively metabolized to several inactive metabolites in vitro via cytochrome P450 (CYP) enzymes 3A4, CYP2C19, and CYP1A2, and to a lesser extent by CYP2D6 and CYP2C9.

Excretion

The pathways of elimination of bortezomib have not been characterized in humans.

Specific Populations

No clinically significant differences in the pharmacokinetics of bortezomib were observed based on age, sex, or renal impairment (including patients administered VELCADE after dialysis). The effect of race on bortezomib pharmacokinetics is unknown.

Patients with Hepatic Impairment

Following administration of bortezomib doses ranging from 0.5 to 1.3 mg/m^2, mild (total bilirubin ≤1× ULN and AST >ULN, or total bilirubin >1 to 1.5× ULN and any AST) hepatic impairment did not alter dose-normalized bortezomib AUC when compared to patients with normal hepatic function. Dose normalized mean bortezomib AUC increased by approximately 60% in patients with moderate (total bilirubin >1.5 to 3× ULN and any AST) or severe (total bilirubin >3× ULN and any AST) hepatic impairment. A lower starting dose is recommended in patients with moderate or severe hepatic impairment.

Drug Interaction Studies

Clinical Studies

No clinically significant differences in bortezomib pharmacokinetics were observed when coadministered with dexamethasone (weak CYP3A4 inducer), omeprazole (strong CYP2C19 inhibitor), or melphalan in combination with prednisone.

Strong CYP3A4 Inhibitor

Coadministration with ketoconazole (strong CYP3A4 inhibitor) increased bortezomib exposure by 35%.

Strong CYP3A4 Inducer

Coadministration with rifampin (strong CYP3A4 inducer) decreased bortezomib exposure by approximately 45%.

In Vitro Studies

Bortezomib may inhibit CYP2C19 activity and increase exposure to drugs that are substrates for this enzyme.

13 NONCLINICAL TOXICOLOGY

13.1 Carcinogenesis, Mutagenesis, Impairment of Fertility

Carcinogenicity studies have not been conducted with bortezomib.

Bortezomib showed clastogenic activity (structural chromosomal aberrations) in the in vitro chromosomal aberration assay using Chinese hamster ovary cells. Bortezomib was not genotoxic when tested in the in vitro mutagenicity assay (Ames test) and in vivo micronucleus assay in mice.

Fertility studies with bortezomib were not performed but evaluation of reproductive tissues has been performed in the general toxicity studies. In the six month rat toxicity study, degenerative effects in the ovary were observed at doses ≥0.3 mg/m^2 (one-fourth of the recommended clinical dose), and degenerative changes in the testes occurred at 1.2 mg/m^2.

13.2 Animal Toxicology and/or Pharmacology

Cardiovascular Toxicity

Studies in monkeys showed that administration of dosages approximately twice the recommended clinical dose resulted in heart rate elevations, followed by profound progressive hypotension, bradycardia, and death 12 to 14 hours postdose. Doses ≥1.2 mg/m^2 induced dose-proportional changes in cardiac parameters. Bortezomib has been shown to distribute to most tissues in the body, including the myocardium. In a repeated dosing toxicity study in the monkey, myocardial hemorrhage, inflammation, and necrosis were also observed.

Chronic Administration

In animal studies at a dose and schedule similar to that recommended for patients (twice weekly dosing for two weeks followed by one week rest), toxicities observed included severe anemia and thrombocytopenia, and gastrointestinal, neurological and lymphoid system toxicities. Neurotoxic effects of bortezomib in animal studies included axonal swelling and degeneration in peripheral nerves, dorsal spinal roots, and tracts of the spinal cord. Additionally, multifocal hemorrhage and necrosis in the brain, eye, and heart were observed.

14 CLINICAL STUDIES

14.1 Multiple Myeloma

Randomized, Open-Label Clinical Study in Patients with Previously Untreated Multiple Myeloma

A prospective, international, randomized (1:1), open-label clinical study (NCT00111319) of 682 patients was conducted to determine whether VELCADE administered intravenously (1.3 mg/m^2) in combination with melphalan (9 mg/m^2) and prednisone (60 mg/m^2) resulted in improvement in time to progression (TTP) when compared to melphalan (9 mg/m^2) and prednisone (60 mg/m^2) in patients with previously untreated multiple myeloma. Treatment was administered for a maximum of nine cycles (approximately 54 weeks) and was discontinued early for disease progression or unacceptable toxicity. Antiviral prophylaxis was recommended for patients on the VELCADE study arm.

The median age of the patients in the study was 71 years (48;91), 50% were male, 88% were Caucasian and the median Karnofsky performance status score for the patients was 80 (60;100). Patients had IgG/IgA/Light chain myeloma in 63%/25%/8% instances, a median hemoglobin of 105 g/L (64;165), and a median platelet count of 221,500/microliter (33,000;587,000).

Efficacy results for the trial are presented in Table 14. At a prespecified interim analysis (with median follow-up of 16.3 months), the combination of VELCADE, melphalan and prednisone therapy resulted in significantly superior results for time to progression, progression-free survival, overall survival and response rate. Further enrollment was halted, and patients receiving melphalan and prednisone were offered VELCADE in addition. A later, prespecified analysis of overall survival (with median follow-up of 36.7 months with a hazard ratio of 0.65, 95% CI: 0.51, 0.84) resulted in a statistically significant survival benefit for the VELCADE, melphalan and prednisone treatment arm despite subsequent therapies including VELCADE based regimens. In an updated analysis of overall survival based on 387 deaths (median follow-up 60.1 months), the median overall survival for the VELCADE, melphalan and prednisone treatment arm was 56.4 months and for the melphalan and prednisone treatment arm was 43.1 months, with a hazard ratio of 0.695 (95% CI: 0.57, 0.85).

Table 14: Summary of Efficacy Analyses in the Previously Untreated Multiple Myeloma Study
Efficacy Endpoint | VELCADE, Melphalan and Prednisone (n=344) | Melphalan and Prednisone (n=338)
Note: All results are based on the analysis performed at a median follow-up duration of 16.3 months except for the overall survival analysis.
Time to Progression
Events n (%) | 101 (29) | 152 (45)
Median [Kaplan-Meier estimate] (months) (95% CI) | 20.7 (17.6, 24.7) | 15.0 (14.1, 17.9)
Hazard ratio [Hazard ratio estimate is based on a Cox proportional-hazard model adjusted for stratification factors: beta2-microglobulin, albumin, and region. A hazard ratio less than one indicates an advantage for VELCADE, melphalan and prednisone] (95% CI) | 0.54 (0.42, 0.70)
p-value [p-value based on the stratified log-rank test adjusted for stratification factors: beta2-microglobulin, albumin, and region] | 0.000002
Progression-Free Survival
Events n (%) | 135 (39) | 190 (56)
Median (months) (95% CI) | 18.3 (16.6, 21.7) | 14.0 (11.1, 15.0)
Hazard ratio (95% CI) | 0.61 (0.49, 0.76)
p-value | 0.00001
Response Rate
CR [EBMT criteria] n (%) | 102 (30) | 12 (4)
PR n (%) | 136 (40) | 103 (30)
nCR n (%) | 5 (1) | 0
CR + PR n (%) | 238 (69) | 115 (34)
p-value [p-value for Response Rate (CR + PR) from the Cochran-Mantel-Haenszel chi-square test adjusted for the stratification factors] | <10^-10
Overall Survival at Median Follow-Up of 36.7 Months
Events (deaths) n (%) | 109 (32) | 148 (44)
Median (months) (95% CI) | Not Reached (46.2, NR) | 43.1 (34.8, NR)
Hazard ratio (95% CI) | 0.65 (0.51, 0.84)
p-value | 0.00084

TTP was statistically significantly longer on the VELCADE, melphalan and prednisone arm (see Figure 1). (median follow-up 16.3 months)

Figure 1: Time to Progression VELCADE, Melphalan and Prednisone vs Melphalan and Prednisone

Overall survival was statistically significantly longer on the VELCADE, melphalan and prednisone arm (see Figure 2). (median follow-up 60.1 months)

Figure 2: Overall Survival VELCADE, Melphalan and Prednisone vs Melphalan and Prednisone

Randomized, Clinical Study in Relapsed Multiple Myeloma of VELCADE vs Dexamethasone

A prospective Phase 3, international, randomized (1:1), stratified, open-label clinical study (NCT00048230) enrolling 669 patients was designed to determine whether VELCADE resulted in improvement in time to progression (TTP) compared to high-dose dexamethasone in patients with progressive multiple myeloma following 1 to 3 prior therapies. Patients considered to be refractory to prior high-dose dexamethasone were excluded as were those with baseline Grade ≥2 peripheral neuropathy or platelet counts <50,000/µL. A total of 627 patients were evaluable for response.

Stratification factors were based on the number of lines of prior therapy the patient had previously received (one previous line vs more than one line of therapy), time of progression relative to prior treatment (progression during or within six months of stopping their most recent therapy vs relapse >6 months after receiving their most recent therapy), and screening beta2-microglobulin levels (≤2.5 mg/L vs >2.5 mg/L).

Baseline patient and disease characteristics are summarized in Table 15.

Table 15: Summary of Baseline Patient and Disease Characteristics in the Relapsed Multiple Myeloma Study
Patient Characteristics | VELCADE (N=333) | Dexamethasone (N=336)
Median age in years (range) | 62.0 (33, 84) | 61.0 (27, 86)
Gender: Male/female | 56%/44% | 60%/40%
Race: Caucasian/black/other | 90%/6%/4% | 88%/7%/5%
Karnofsky performance status score ≤70 | 13% | 17%
Hemoglobin <100 g/L | 32% | 28%
Platelet count <75 × 10^9/L | 6% | 4%
Disease Characteristics
Type of myeloma (%): IgG/IgA/Light chain | 60%/23%/12% | 59%/24%/13%
Median beta2-microglobulin (mg/L) | 3.7 | 3.6
Median albumin (g/L) | 39.0 | 39.0
Creatinine clearance ≤30 mL/min [n (%)] | 17 (5%) | 11 (3%)
Median Duration of Multiple Myeloma Since Diagnosis (Years) | 3.5 | 3.1
Number of Prior Therapeutic Lines of Treatment
Median | 2 | 2
1 prior line | 40% | 35%
>1 prior line | 60% | 65%
Previous Therapy
Any prior steroids, e.g., dexamethasone, VAD | 98% | 99%
Any prior anthracyclines, e.g., VAD, mitoxantrone | 77% | 76%
Any prior alkylating agents, e.g., MP, VBMCP | 91% | 92%
Any prior thalidomide therapy | 48% | 50%
Vinca alkaloids | 74% | 72%
Prior stem cell transplant/other high-dose therapy | 67% | 68%
Prior experimental or other types of therapy | 3% | 2%

Patients in the VELCADE treatment group were to receive 8, three week treatment cycles followed by 3, five week treatment cycles of VELCADE. Patients achieving a CR were treated for four cycles beyond first evidence of CR. Within each three week treatment cycle, VELCADE 1.3 mg/m^2/dose alone was administered by intravenous bolus twice weekly for two weeks on Days 1, 4, 8, and 11 followed by a ten day rest period (Days 12 to 21). Within each five week treatment cycle, VELCADE 1.3 mg/m^2/dose alone was administered by intravenous bolus once weekly for four weeks on Days 1, 8, 15, and 22 followed by a 13 day rest period (Days 23 to 35) [see Dosage and Administration (2.2)].

Patients in the dexamethasone treatment group were to receive 4, five week treatment cycles followed by 5, four week treatment cycles. Within each five week treatment cycle, dexamethasone 40 mg/day PO was administered once daily on Days 1 to 4, 9 to 12, and 17 to 20 followed by a 15 day rest period (Days 21 to 35). Within each four week treatment cycle, dexamethasone 40 mg/day PO was administered once daily on Days 1 to 4 followed by a 24 day rest period (Days 5 to 28). Patients with documented progressive disease on dexamethasone were offered VELCADE at a standard dose and schedule on a companion study. Following a preplanned interim analysis of time to progression, the dexamethasone arm was halted and all patients randomized to dexamethasone were offered VELCADE, regardless of disease status.

In the VELCADE arm, 34% of patients received at least one VELCADE dose in all eight of the three week cycles of therapy, and 13% received at least one dose in all 11 cycles. The average number of VELCADE doses during the study was 22, with a range of 1 to 44. In the dexamethasone arm, 40% of patients received at least one dose in all four of the five week treatment cycles of therapy, and 6% received at least one dose in all nine cycles.

The time to event analyses and response rates from the relapsed multiple myeloma study are presented in Table 16. Response and progression were assessed using the European Group for Blood and Marrow Transplantation (EBMT) criteria. Complete response (CR) required <5% plasma cells in the marrow, 100% reduction in M-protein, and a negative immunofixation test (IF^-). Partial response (PR) requires ≥50% reduction in serum myeloma protein and ≥90% reduction of urine myeloma protein on at least two occasions for a minimum of at least six weeks along with stable bone disease and normal calcium. Near complete response (nCR) was defined as meeting all the criteria for complete response including 100% reduction in M-protein by protein electrophoresis; however, M-protein was still detectable by immunofixation (IF^+).

Table 16: Summary of Efficacy Analyses in the Relapsed Multiple Myeloma Study
Efficacy Endpoint | All Patients |  | 1 Prior Line of Therapy |  | >1 Prior Line of Therapy
Efficacy Endpoint | VELCADE | Dex | VELCADE | Dex | VELCADE | Dex
Efficacy Endpoint | (n=333) | (n=336) | (n=132) | (n=119) | (n=200) | (n=217)
Time to Progression Events n (%) | 147 (44) | 196 (58) | 55 (42) | 64 (54) | 92 (46) | 132 (61)
Median [Kaplan-Meier estimate] (95% CI) | 6.2 mo (4.9, 6.9) | 3.5 mo (2.9, 4.2) | 7.0 mo (6.2, 8.8) | 5.6 mo (3.4, 6.3) | 4.9 mo (4.2, 6.3) | 2.9 mo (2.8, 3.5)
Hazard ratio [Hazard ratio is based on Cox proportional-hazard model with the treatment as single independent variable. A hazard ratio less than one indicates an advantage for VELCADE] (95% CI) | 0.55 (0.44, 0.69) |  | 0.55 (0.38, 0.81) |  | 0.54 (0.41, 0.72)
p-value [p-value based on the stratified log-rank test including randomization stratification factors] | <0.0001 |  | 0.0019 |  | <0.0001
Overall Survival Events (deaths) n (%) | 51 (15) | 84 (25) | 12 (9) | 24 (20) | 39 (20) | 60 (28)
Hazard ratio (95% CI) | 0.57 (0.40, 0.81) |  | 0.39 (0.19, 0.81) |  | 0.65 (0.43, 0.97)
p-value, [Precise p-value cannot be rendered] | <0.05 |  | <0.05 |  | <0.05
Response Rate Population [Response population includes patients who had measurable disease at baseline and received at least one dose of study drug] n=627 | n=315 | n=312 | n=128 | n=110 | n=187 | n=202
CR [EBMT criteria; nCR meets all EBMT criteria for CR but has positive IF. Under EBMT criteria nCR is in the PR category] n (%) | 20 (6) | 2 (<1) | 8 (6) | 2 (2) | 12 (6) | 0 (0)
PR n(%) | 101 (32) | 54 (17) | 49 (38) | 27 (25) | 52 (28) | 27 (13)
nCR, [In two patients, the IF was unknown] n(%) | 21 (7) | 3 (<1) | 8 (6) | 2 (2) | 13 (7) | 1 (<1)
CR + PR n (%) | 121 (38) | 56 (18) | 57 (45) | 29 (26) | 64 (34) | 27 (13)
p-value [p-value for Response Rate (CR + PR) from the Cochran-Mantel-Haenszel chi-square test adjusted for the stratification factors] | <0.0001 |  | 0.0035 |  | <0.0001

TTP was statistically significantly longer on the VELCADE arm (see Figure 3).

Figure 3: Time to Progression Bortezomib vs Dexamethasone (Relapsed Multiple Myeloma Study)

As shown in Figure 4, VELCADE had a significant survival advantage relative to dexamethasone (p <0.05). The median follow-up was 8.3 months.

Figure 4: Overall Survival Bortezomib vs Dexamethasone (Relapsed Multiple Myeloma Study)

For the 121 patients achieving a response (CR or PR) on the VELCADE arm, the median duration was 8.0 months (95% CI: 6.9, 11.5 months) compared to 5.6 months (95% CI: 4.8, 9.2 months) for the 56 responders on the dexamethasone arm. The response rate was significantly higher on the VELCADE arm regardless of beta2-microglobulin levels at baseline.

Randomized, Open-Label Clinical Study of VELCADE Subcutaneous vs Intravenous in Relapsed Multiple Myeloma

An open-label, randomized, Phase 3 noninferiority study (NCT00722566) compared the efficacy and safety of the subcutaneous administration of VELCADE vs the intravenous administration. This study included 222 bortezomib naïve patients with relapsed multiple myeloma, who were randomized in a 2:1 ratio to receive 1.3 mg/m^2 of VELCADE by either the subcutaneous (n=148) or intravenous (n=74) route for eight cycles. Patients who did not obtain an optimal response (less than Complete Response (CR)) to therapy with VELCADE alone after four cycles were allowed to receive oral dexamethasone 20 mg daily on the day of and after VELCADE administration (82 patients in subcutaneous treatment group and 39 patients in the intravenous treatment group). Patients with baseline Grade ≥2 peripheral neuropathy or neuropathic pain, or platelet counts <50,000/µL were excluded. A total of 218 patients were evaluable for response.

Stratification factors were based on the number of lines of prior therapy the patient had received (one previous line vs more than one line of therapy), and international staging system (ISS) stage (incorporating beta2-microglobulin and albumin levels; Stages I, II, or III).

The baseline demographic and other characteristics of the two treatment groups are summarized as follows: the median age of the patient population was approximately 64 years of age (range: 38 to 88 years), primarily male (subcutaneous: 50%, intravenous: 64%); the primary type of myeloma is IgG (subcutaneous: 65% IgG, 26% IgA, 8% light chain; intravenous: 72% IgG, 19% IgA, 8% light chain), ISS staging I/II/III (%) was 27, 41, 32 for both subcutaneous and intravenous, Karnofsky performance status score was ≤70% in 22% of subcutaneous and 16% of intravenous, creatinine clearance was 67.5 mL/min in subcutaneous and 73 mL/min in intravenous, the median years from diagnosis was 2.68 and 2.93 in subcutaneous and intravenous respectively and the proportion of patients with more than one prior line of therapy was 38% in subcutaneous and 35% in intravenous.

This study met its primary (noninferiority) objective that single agent subcutaneous VELCADE retains at least 60% of the overall response rate after four cycles relative to single agent intravenous VELCADE. The results are provided in Table 17.

Table 17: Summary of Efficacy Analyses in the Relapsed Multiple Myeloma Study of VELCADE Subcutaneous vs Intravenous
 | Subcutaneous VELCADE | Intravenous VELCADE
Intent to Treat Population | (n=148) | (n=74)
Primary Endpoint
Response Rate at 4 Cycles
ORR (CR + PR) n(%) | 63 (43) | 31 (42)
Ratio of Response Rates (95% CI) | 1.01 (0.73, 1.40)
CR n (%) | 11 (7) | 6 (8)
PR n (%) | 52 (35) | 25 (34)
nCR n (%) | 9 (6) | 4 (5)
Secondary Endpoints
Response Rate at 8 Cycles
ORR (CR + PR) | 78 (53) | 38 (51)
CR n (%) | 17 (11) | 9 (12)
PR n (%) | 61 (41) | 29 (39)
nCR n (%) | 14 (9) | 7 (9)
Median Time to Progression, months | 10.4 | 9.4
Median Progression-Free Survival, months | 10.2 | 8.0
1 Year Overall Survival (%) [Median duration of follow-up is 11.8 months] | 72.6 | 76.7

A Randomized, Phase 2 Dose-Response Study in Relapsed Multiple Myeloma

An open-label, multicenter study randomized 54 patients with multiple myeloma who had progressed or relapsed on or after front-line therapy to receive VELCADE 1 mg/m^2 or 1.3 mg/m^2 intravenous bolus twice weekly for two weeks on Days 1, 4, 8, and 11 followed by a ten day rest period (Days 12 to 21). The median duration of time between diagnosis of multiple myeloma and first dose of VELCADE on this trial was two years, and patients had received a median of one prior line of treatment (median of three prior therapies). A single complete response was seen at each dose. The overall response rates (CR + PR) were 30% (8/27) at 1 mg/m^2 and 38% (10/26) at 1.3 mg/m^2.

A Phase 2 Open-Label Extension Study in Relapsed Multiple Myeloma

Patients from the two Phase 2 studies, who in the investigators' opinion would experience additional clinical benefit, continued to receive VELCADE beyond 8 cycles on an extension study. Sixty-three (63) patients from the Phase 2 multiple myeloma studies were enrolled and received a median of seven additional cycles of VELCADE therapy for a total median of 14 cycles (range: 7 to 32). The overall median dosing intensity was the same in both the parent protocol and extension study. Sixty-seven percent (67%) of patients initiated the extension study at the same or higher dose intensity at which they completed the parent protocol, and 89% of patients maintained the standard three week dosing schedule during the extension study. No new cumulative or new long-term toxicities were observed with prolonged VELCADE treatment [see Adverse Reactions (6.1)].

A Single-Arm Trial of Retreatment in Relapsed Multiple Myeloma

A single-arm, open-label trial (NCT00431769) was conducted to determine the efficacy and safety of retreatment with VELCADE. One hundred and thirty patients (≥18 years of age) with multiple myeloma who previously had at least partial response on a VELCADE-containing regimen (median of two prior lines of therapy [range: 1 to 7]) were retreated upon progression with VELCADE administered intravenously. Patients were excluded from trial participation if they had peripheral neuropathy or neuropathic pain of Grade ≥2. At least six months after prior VELCADE therapy, VELCADE was restarted at the last tolerated dose of 1.3 mg/m^2 (n=93) or ≤1 mg/m^2 (n=37) and given on Days 1, 4, 8 and 11 every three weeks for maximum of eight cycles either as single agent or in combination with dexamethasone in accordance with the standard of care. Dexamethasone was administered in combination with VELCADE to 83 patients in Cycle 1 with an additional 11 patients receiving dexamethasone during the course of VELCADE retreatment cycles.

The primary endpoint was best confirmed response to retreatment as assessed by European Group for Blood and Marrow Transplantation (EBMT) criteria. Fifty of the 130 patients achieved a best confirmed response of Partial Response or better for an overall response rate of 38.5% (95% CI: 30.1, 47.4). One patient achieved a Complete Response and 49 achieved Partial Response. In the 50 responding patients, the median duration of response was 6.5 months and the range was 0.6 to 19.3 months.

14.2 Mantle Cell Lymphoma

A Randomized, Open-Label Clinical Study in Patients with Previously Untreated Mantle Cell Lymphoma

A randomized, open-label, Phase 3 study (NCT00722137) was conducted in 487 adult patients with previously untreated mantle cell lymphoma (Stage II, III or IV) who were ineligible or not considered for bone marrow transplantation to determine whether VELCADE administered in combination with rituximab, cyclophosphamide, doxorubicin, and prednisone (VcR-CAP) resulted in improvement in progression-free survival (PFS) when compared to the combination of rituximab, cyclophosphamide, doxorubicin, vincristine, and prednisone (R-CHOP). This clinical study utilized independent pathology confirmation and independent radiologic response assessment.

Patients in the VcR-CAP treatment arm received VELCADE (1.3 mg/m^2) administered intravenously on Days 1, 4, 8, and 11 (rest period Days 12 to 21); rituximab (375 mg/m^2) on Day 1; cyclophosphamide (750 mg/m^2) on Day 1; doxorubicin (50 mg/m^2) on Day 1; and prednisone (100 mg/m^2) on Day 1 through Day 5 of the 21 day treatment cycle. For patients with a response first documented at Cycle 6, two additional treatment cycles were allowed.

Median patient age was 66 years, 74% were male, 66% were Caucasian and 32% were Asian. Sixty-nine percent of patients had a positive bone marrow aspirate and/or a positive bone marrow biopsy for MCL, 54% of patients had an International Prognostic Index (IPI) score of three (high-intermediate) or higher and 76% had Stage IV disease.

The majority of the patients in both groups received six or more cycles of treatment, 84% in the VcR-CAP group and 83% in the R-CHOP group. Median number of cycles received by patients in both treatment arms was six with 17% of patients in the R-CHOP group and 14% of subjects in the VcR-CAP group receiving up to two additional cycles.

The efficacy results for PFS, CR and ORR with a median follow-up of 40 months are presented in Table 18. The response criteria used to assess efficacy were based on the International Workshop to Standardize Response Criteria for Non-Hodgkin's Lymphoma (IWRC). Final overall survival results at a median follow-up of 78.5 months are also presented in Table 18 and Figure 6. The combination of VcR-CAP resulted in statistically significant prolongation of PFS compared with R-CHOP (see Table 18, Figure 5).

Table 18: Summary of Efficacy Analyses in the Previously Untreated Mantle Cell Lymphoma Study
Efficacy Endpoint n: Intent to Treat patients | VcR-CAP (n=243) | R-CHOP (n=244)
Note: All results are based on the analysis performed at a median follow-up duration of 40 months except for the overall survival analysis, which was performed at a median follow-up of 78.5 months.
CI = Confidence Interval; IPI = International Prognostic Index; LDH = Lactate dehydrogenase
Progression-Free Survival (by independent radiographic assessment)
Events n (%) | 133 (55) | 165 (68)
Median [Based on Kaplan-Meier product limit estimates.] (months) (95% CI) | 25 (20, 32) | 14 (12, 17)
Hazard ratio [Hazard ratio estimate is based on a Cox's model stratified by IPI risk and stage of disease. A hazard ratio <1 indicates an advantage for VcR-CAP.] (95% CI) | 0.63 (0.50, 0.79)
p-value [Based on Log rank test stratified with IPI risk and stage of disease.] | <0.001
Complete Response Rate (CR) [Includes CR by independent radiographic assessment, bone marrow, and LDH using ITT population.]
n (%) (95% CI) | 108 (44) (38, 51) | 82 (34) (28, 40)
Overall Response Rate (CR + CRu + PR) [Includes CR + CRu + PR by independent radiographic assessment, regardless of the verification by bone marrow and LDH, using ITT population.]
n (%) | 214 (88) | 208 (85)
(95% CI) | (83, 92) | (80, 89)
Overall Survival
Events n (%) | 103 (42) | 138 (57)
Median (months) (95% CI) | 91 (71, NE) | 56 (47, 69)
Hazard Ratio (95% CI) | 0.66 (0.51, 0.85)

Figure 5: Progression-Free Survival VcR-CAP vs R-CHOP (previously Untreated Mantle Cell Lymphoma Study)

Key: R-CHOP = rituximab, cyclophosphamide, doxorubicin, vincristine, and prednisone; VcR-CAP = VELCADE, rituximab, cyclophosphamide, doxorubicin, and prednisone.

Figure 6: Overall Survival VcR-CAP vs R-CHOP (previously Untreated Mantle Cell Lymphoma Study)

Key: R-CHOP = rituximab, cyclophosphamide, doxorubicin, vincristine, and prednisone; VcR-CAP = VELCADE, rituximab, cyclophosphamide, doxorubicin, and prednisone.

A Phase 2 Single-Arm Clinical Study in Relapsed Mantle Cell Lymphoma after Prior Therapy

The safety and efficacy of VELCADE in relapsed or refractory mantle cell lymphoma were evaluated in an open-label, single-arm, multicenter study (NCT00063713) of 155 patients with progressive disease who had received at least one prior therapy. The median age of the patients was 65 years (42, 89), 81% were male, and 92% were Caucasian. Of the total, 75% had one or more extra-nodal sites of disease, and 77% were Stage 4. In 91% of the patients, prior therapy included all of the following: an anthracycline or mitoxantrone, cyclophosphamide, and rituximab. A total of thirty-seven percent (37%) of patients were refractory to their last prior therapy. An intravenous bolus injection of VELCADE 1.3 mg/m^2/dose was administered twice weekly for two weeks on Days 1, 4, 8, and 11 followed by a ten day rest period (Days 12 to 21) for a maximum of 17 treatment cycles. Patients achieving a CR or CRu were treated for four cycles beyond first evidence of CR or CRu. The study employed dose modifications for toxicity [see Dosage and Administration (2.6, 2.7)].

Responses to VELCADE are shown in Table 19. Response rates to VELCADE were determined according to the International Workshop Response Criteria (IWRC) based on independent radiologic review of CT scans. The median number of cycles administered across all patients was four; in responding patients the median number of cycles was eight. The median time to response was 40 days (range: 31 to 204 days). The median duration of follow-up was more than 13 months.

Table 19: Response Outcomes in a Phase 2 Relapsed Mantle Cell Lymphoma Study
Response Analyses (N=155) | N (%) | 95% CI
Overall Response Rate (IWRC) (CR + CRu + PR) | 48 (31) | (24, 39)
Complete Response (CR + CRu) | 12 (8) | (4, 13)
CR | 10 (6) | (3, 12)
CRu | 2 (1) | (0, 5)
Partial Response (PR) | 36 (23) | (17, 31)
Duration of Response | Median | 95% CI
CR + CRu + PR (N=48) | 9.3 months | (5.4, 13.8)
CR + CRu (N=12) | 15.4 months | (13.4, 15.4)
PR (N=36) | 6.1 months | (4.2, 9.3)

15 REFERENCES

1. "OSHA Hazardous Drugs" (refer to antineoplastic weblinks including OSHA Technical Manual). OSHA. http://www.osha.gov/SLTC/hazardousdrugs/index.html

16 HOW SUPPLIED/STORAGE AND HANDLING

VELCADE® (bortezomib) for Injection is supplied as individually cartoned 10 mL vials containing 3.5 mg of bortezomib as a white to off-white cake or powder.

NDC 63020-049-01
3.5 mg single-dose vial

STORAGE AND HANDLING

Unopened vials may be stored at controlled room temperature 25°C (77°F); excursions permitted from 15°C to 30°C (59°F to 86°F) [see USP Controlled Room Temperature]. Retain in original package to protect from light.

Follow guidelines for handling and disposal for hazardous drugs, including the use of gloves and other protective clothing to prevent skin contact^1.

17 PATIENT COUNSELING INFORMATION

Discuss the following with patients prior to treatment with VELCADE:

Peripheral Neuropathy

Advise patients to report the development or worsening of sensory and motor peripheral neuropathy to their healthcare provider [see Warnings and Precautions (5.1)].

Hypotension

Advise patients to drink adequate fluids to avoid dehydration and to report symptoms of hypotension to their healthcare provider [see Warnings and Precautions (5.2)].

Instruct patients to seek medical advice if they experience symptoms of dizziness, light headedness or fainting spells, or muscle cramps.

Cardiac Toxicity

Advise patients to report signs or symptoms of heart failure to their healthcare provider [see Warnings and Precautions (5.3)].

Pulmonary Toxicity

Advise patients to report symptoms of ARDS, pulmonary hypertension, pneumonitis, and pneumonia immediately to their healthcare provider [see Warnings and Precautions (5.4)].

Posterior Reversible Encephalopathy Syndrome (PRES)

Advise patients to seek immediate medical attention for signs or symptoms of PRES [see Warnings and Precautions (5.5)].

Gastrointestinal Toxicity

Advise patients to report symptoms of gastrointestinal toxicity to their healthcare provider and to drink adequate fluids to avoid dehydration. Instruct patients to seek medical advice if they experience symptoms of dizziness, light headedness or fainting spells, or muscle cramps [see Warnings and Precautions (5.6)].

Thrombocytopenia/Neutropenia

Advise patients to report signs or symptoms of bleeding or infection immediately to their healthcare provider [see Warnings and Precautions (5.7)].

Tumor Lysis Syndrome

Advise patients of the risk of tumor lysis syndrome and to drink adequate fluids to avoid dehydration [see Warnings and Precautions (5.8)].

Hepatic Toxicity

Advise patients to report signs or symptoms of hepatic toxicity to their healthcare provider [see Warnings and Precautions (5.9)].

Thrombotic Microangiopathy

Advise patients to seek immediate medical attention if any signs or symptoms of thrombotic microangiopathy occur [see Warnings and Precautions (5.10)].

Ability to Drive or Operate Machinery or Impairment of Mental Ability

VELCADE may cause fatigue, dizziness, syncope, orthostatic/postural hypotension. Advise patients not to drive or operate machinery if they experience any of these symptoms [see Warnings and Precautions (5.2, 5.5)].

Embryo-Fetal Toxicity

Advise females of the potential risk to the fetus and to use effective contraception during treatment with VELCADE and for seven months following the last dose. Advise male patients with female partners of reproductive potential to use effective contraception during treatment with VELCADE and for four months following the last dose. Instruct patients to report pregnancy to their physicians immediately if they or their female partner becomes pregnant during treatment or within seven months following last dose [see Warnings and Precautions (5.11)].

Lactation

Advise women not to breastfeed while receiving VELCADE and for two months after last dose [see Use in Specific Populations (8.2)].

Concomitant Medications

Advise patients to speak with their physicians about any other medication they are currently taking.

Diabetic Patients

Advise patients to check their blood sugar frequently if using an oral antidiabetic medication and to notify their physicians of any changes in blood sugar level.

Dermal

Advise patients to contact their physicians if they experience rash, severe injection site reactions [see Dosage and Administration (2.9)], or skin pain. Discuss with patients the option for antiviral prophylaxis for herpes virus infection [see Adverse Reactions (6.1)].

Other

Instruct patients to contact their physicians if they develop an increase in blood pressure, bleeding, fever, constipation, or decreased appetite.

Distributed by:
Takeda Pharmaceuticals America, Inc.
Cambridge, MA 02142

VELCADE and are registered trademarks of Millennium Pharmaceuticals, Inc.

©2025 Takeda Pharmaceuticals U.S.A., Inc.

All rights reserved.

VEL347 R24

PRINCIPAL DISPLAY PANEL - 3.5 mg Vial Label

NDC 63020-049-01

VELCADE®
(bortezomib) for Injection

3.5 mg/vial

SINGLE-DOSE VIAL
DISCARD UNUSED PORTION

FOR INTRAVENOUS OR SUBCUTANEOUS USE

PRINCIPAL DISPLAY PANEL - 3.5 mg Vial Carton

See
Reconstitution
Information on Back

NDC 63020-049-01

VELCADE®
(bortezomib) for Injection

3.5 mg/vial

SINGLE-DOSE VIAL – DISCARD UNUSED PORTION

FOR INTRAVENOUS OR SUBCUTANEOUS USE

Takeda